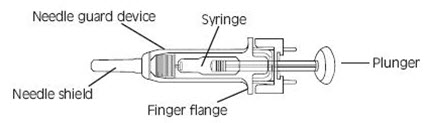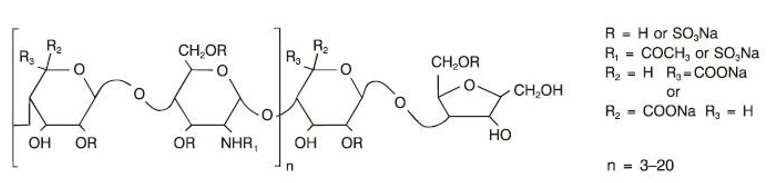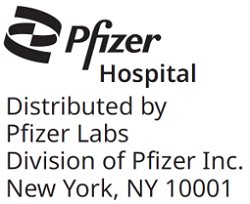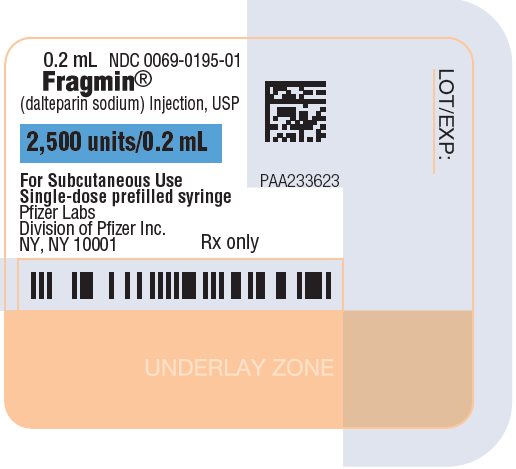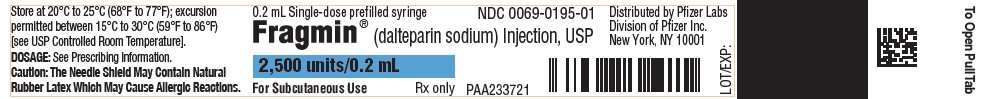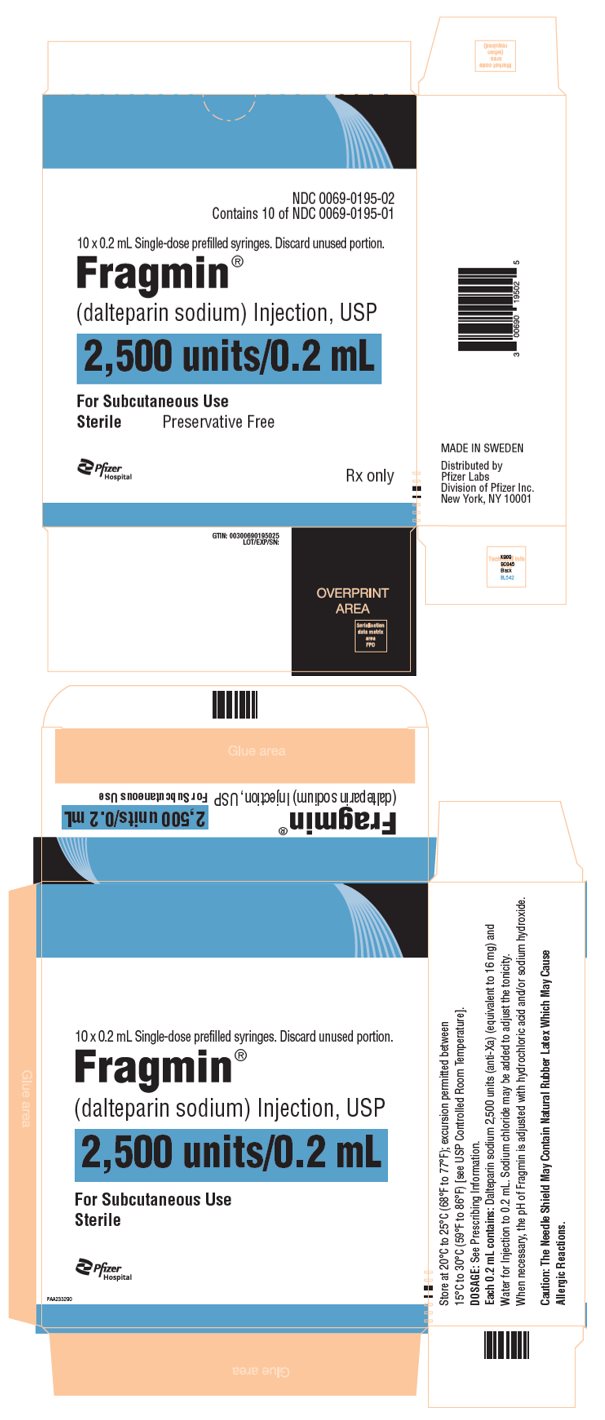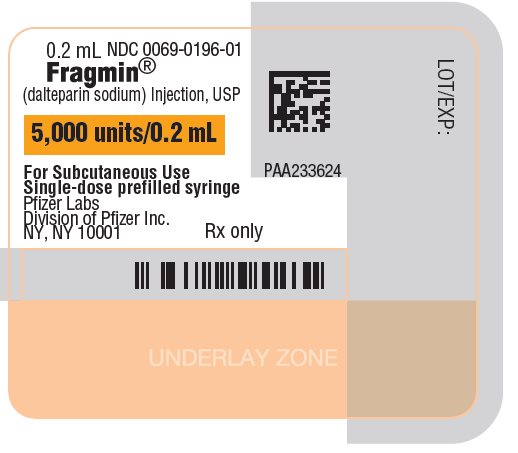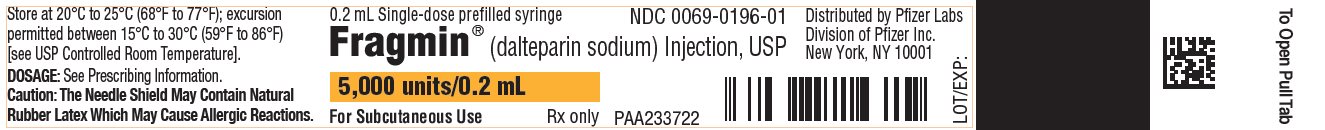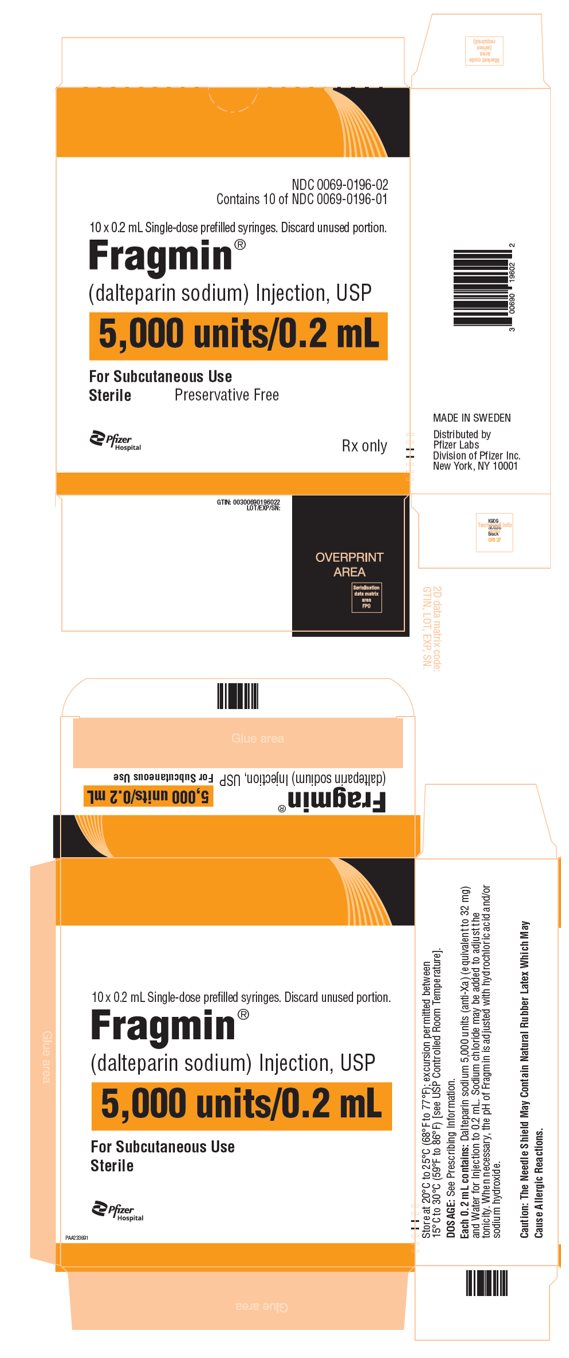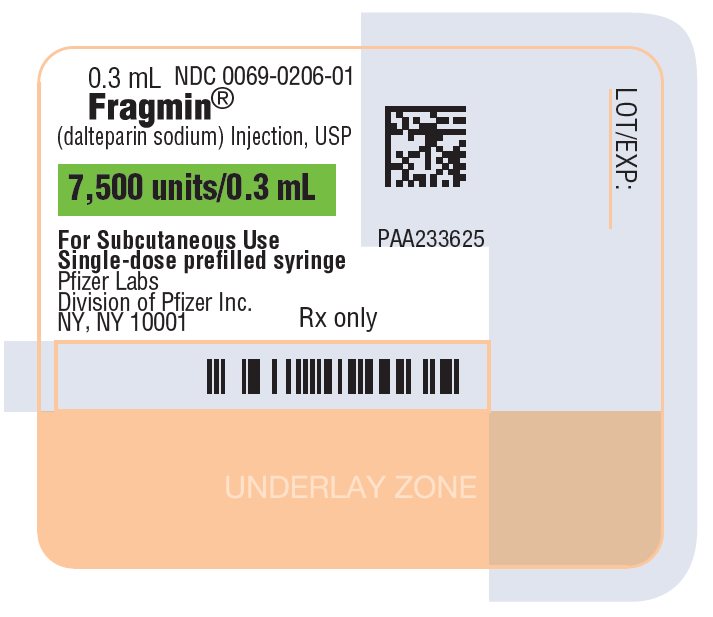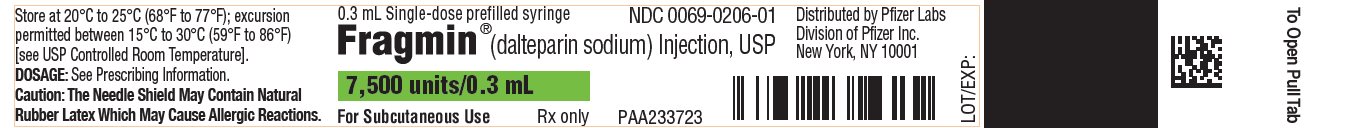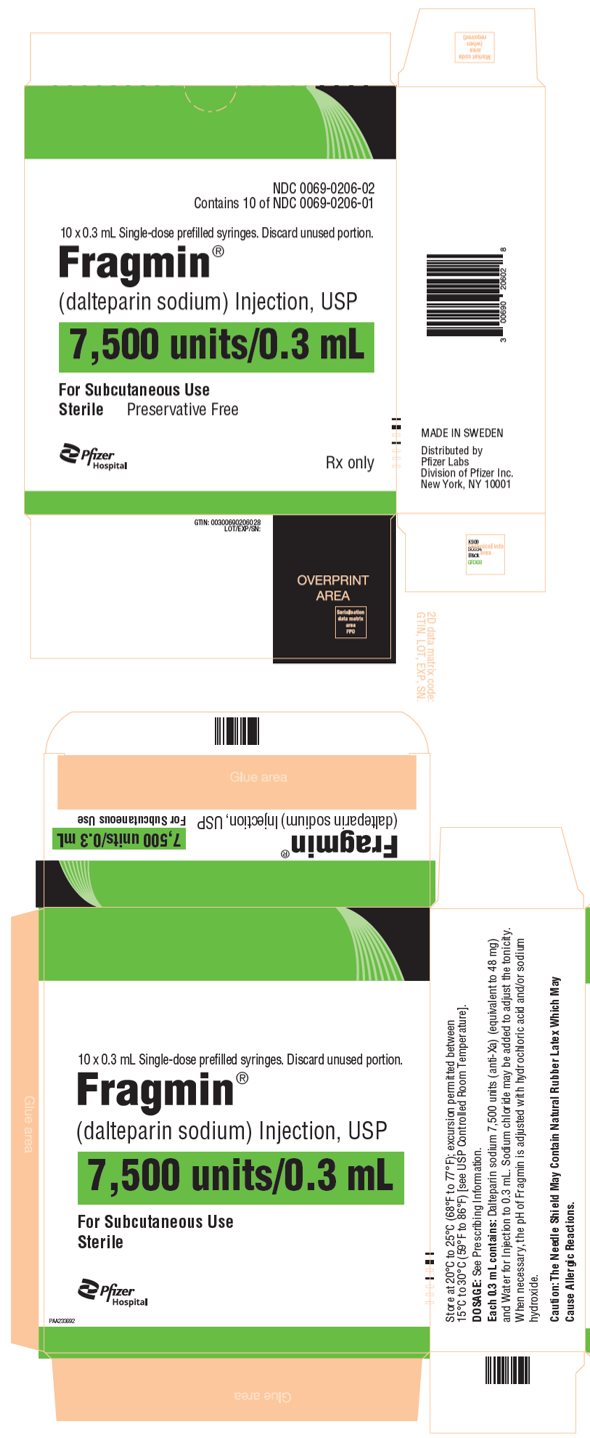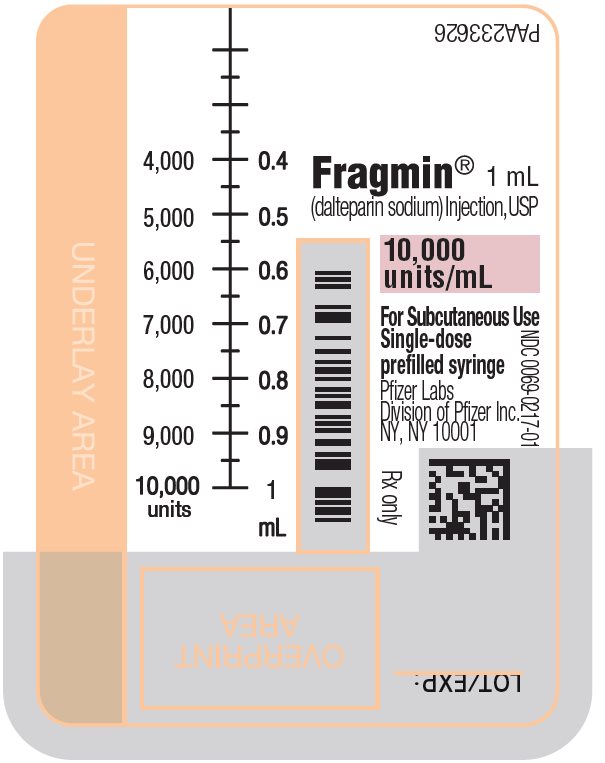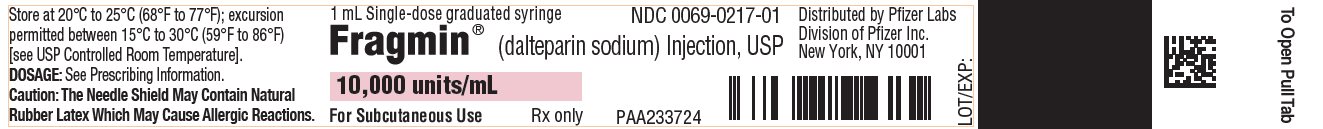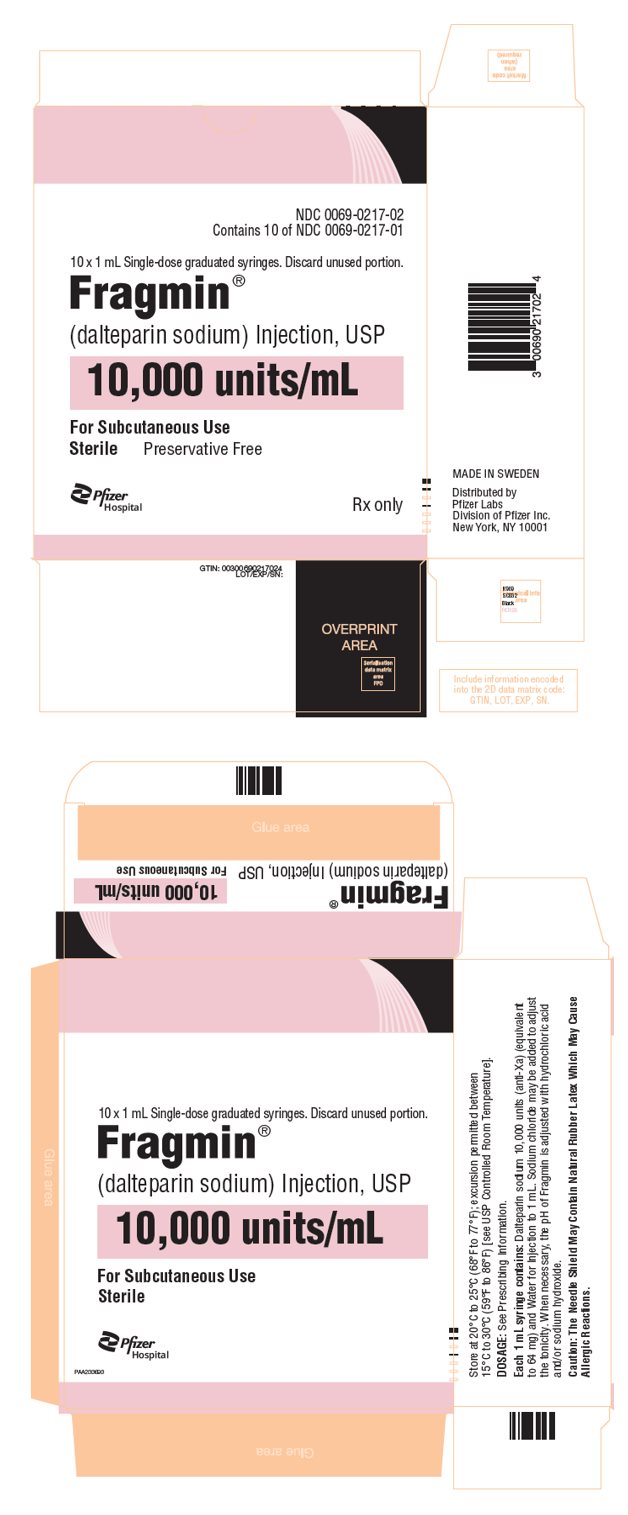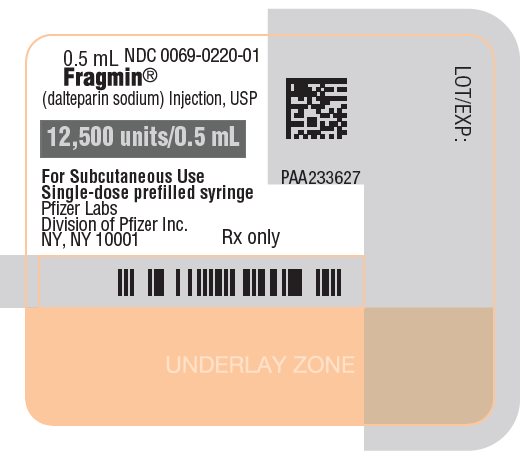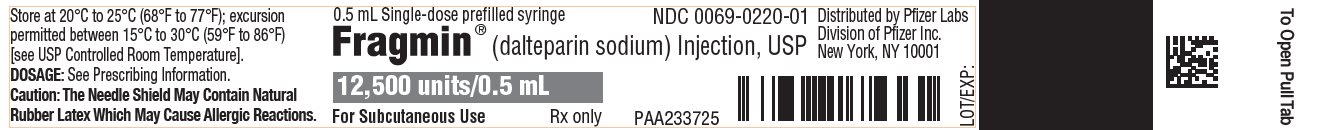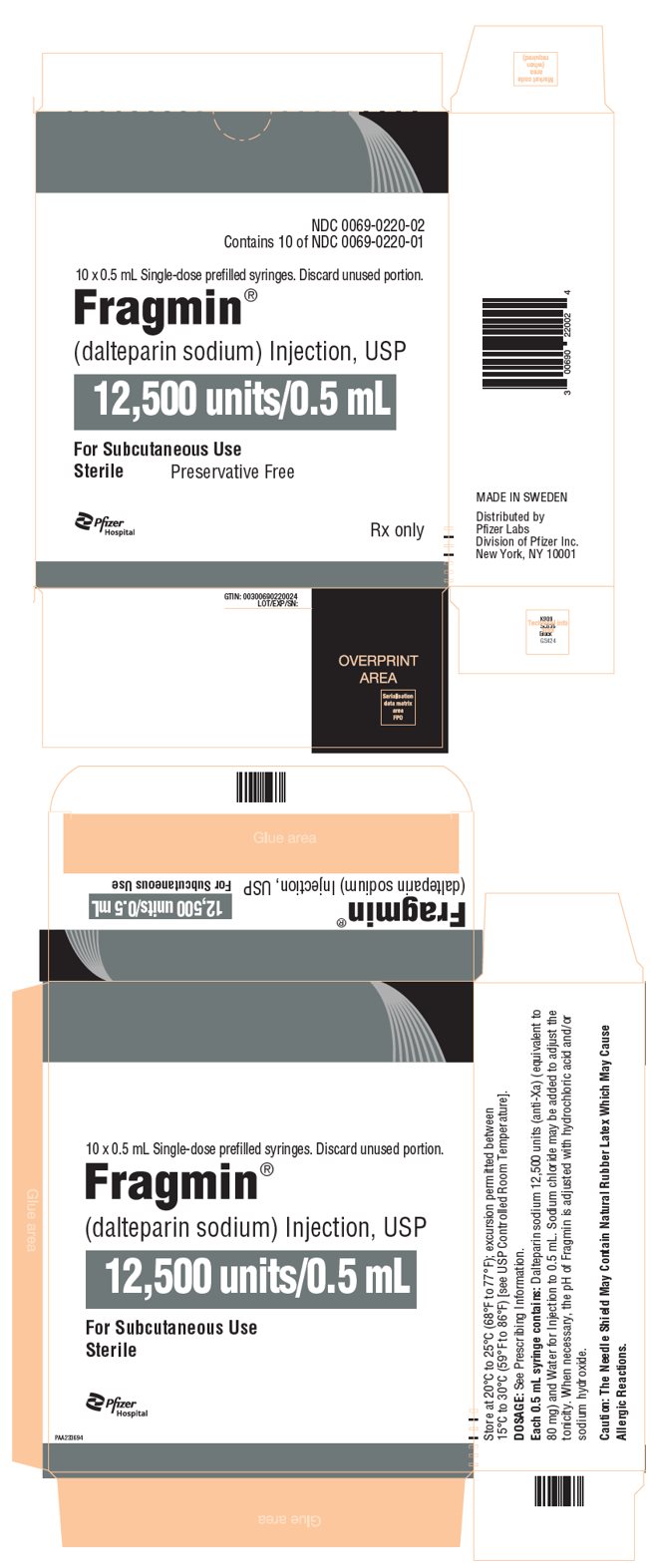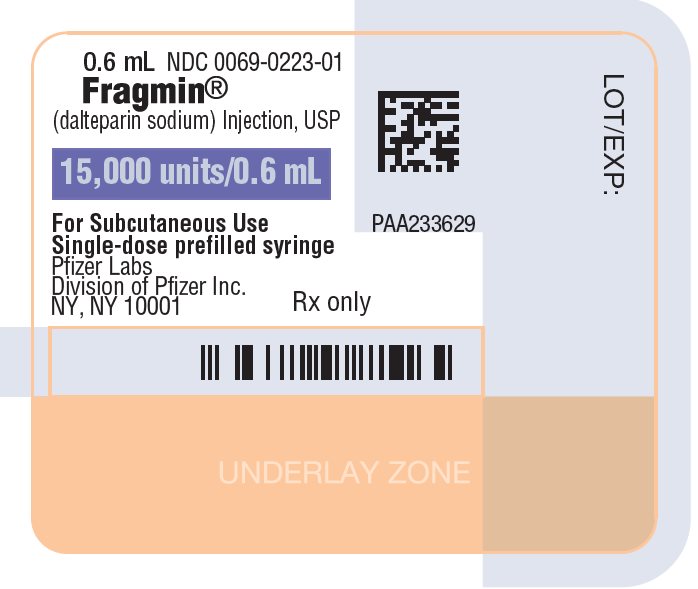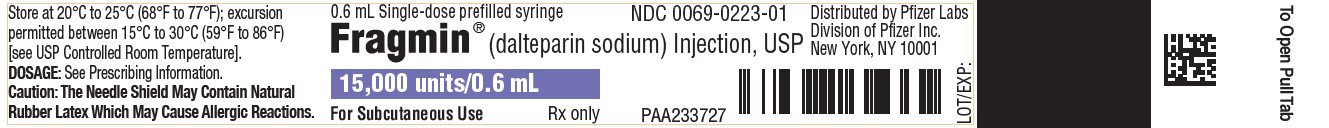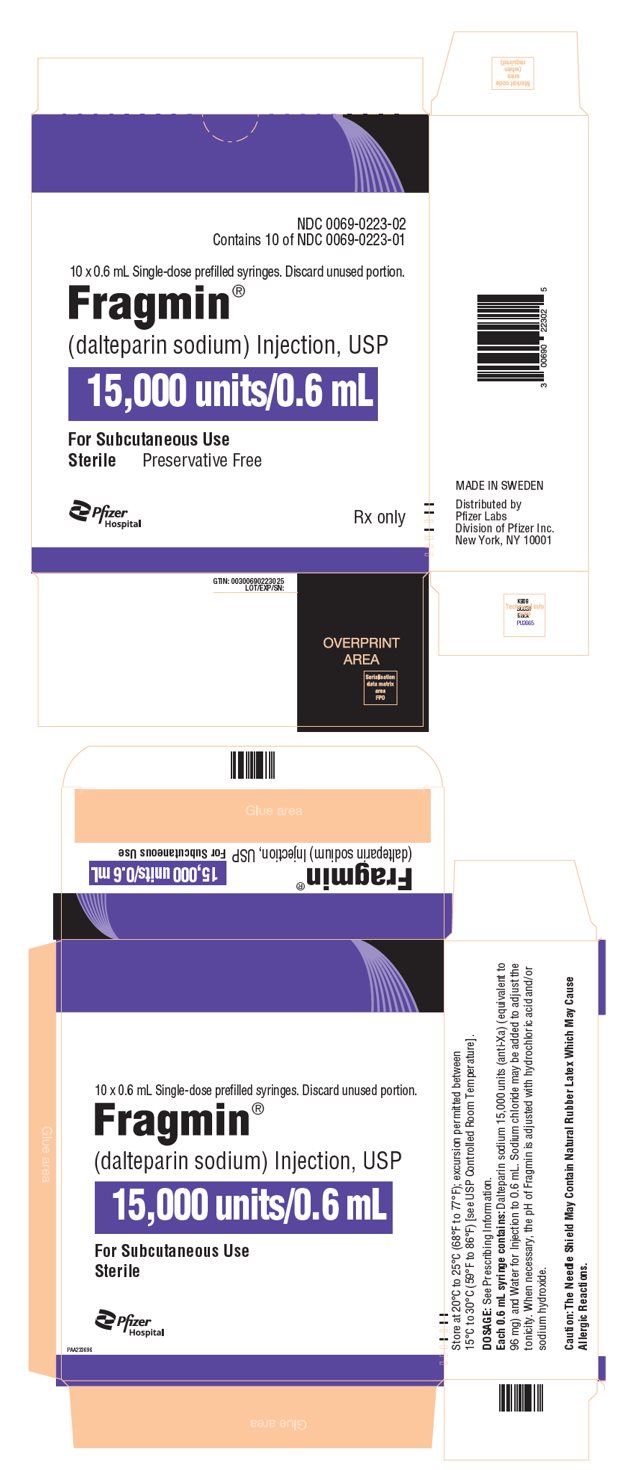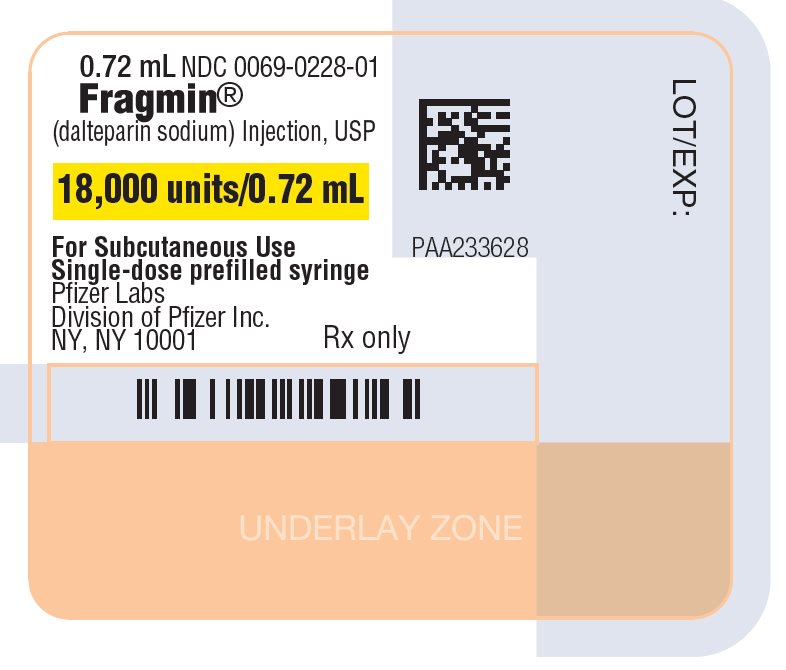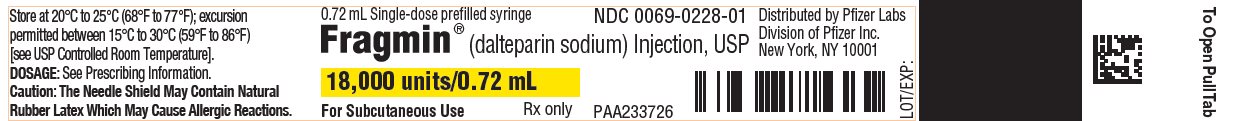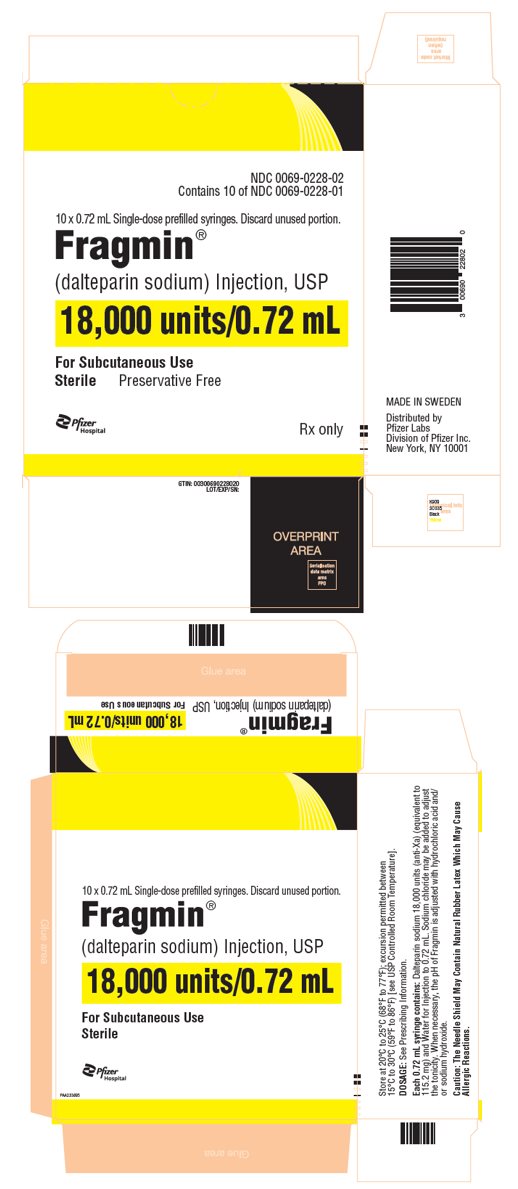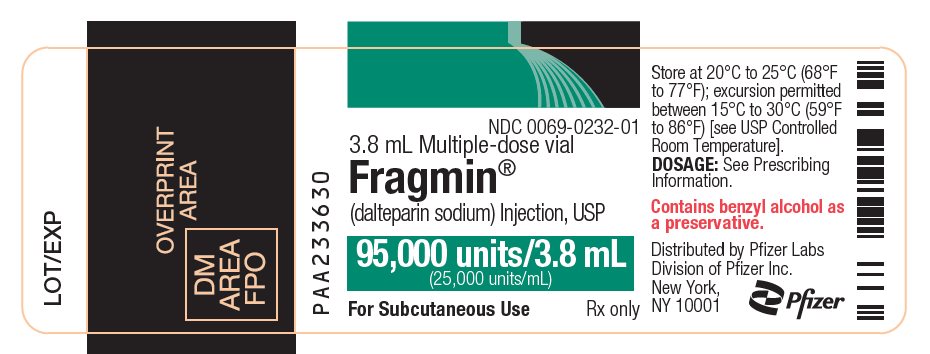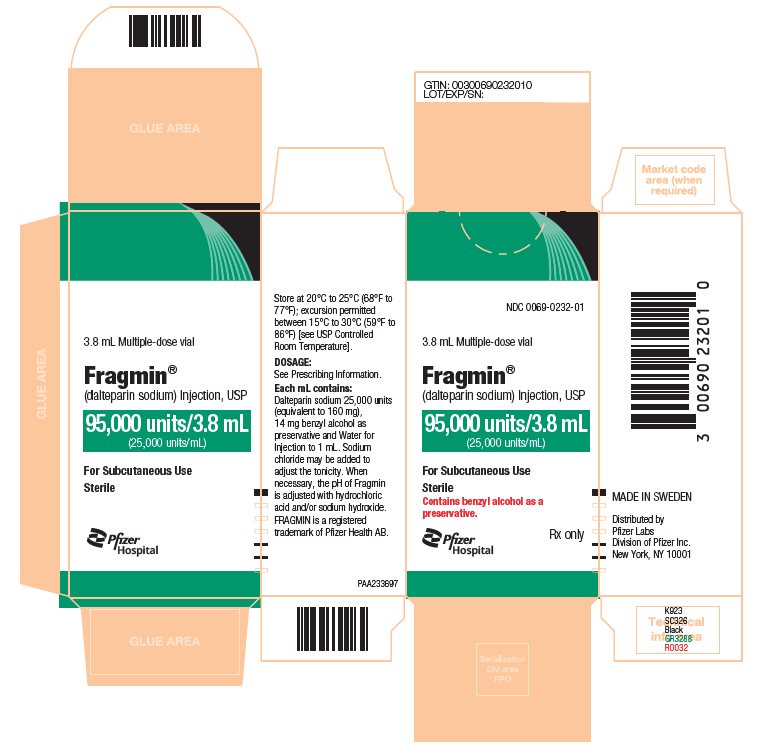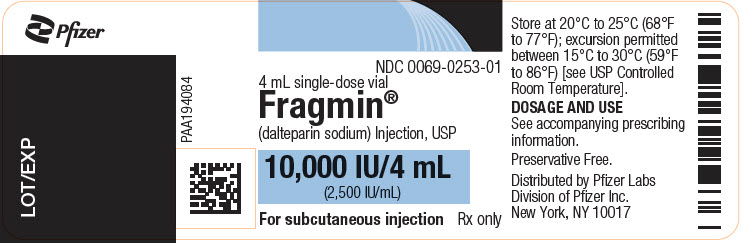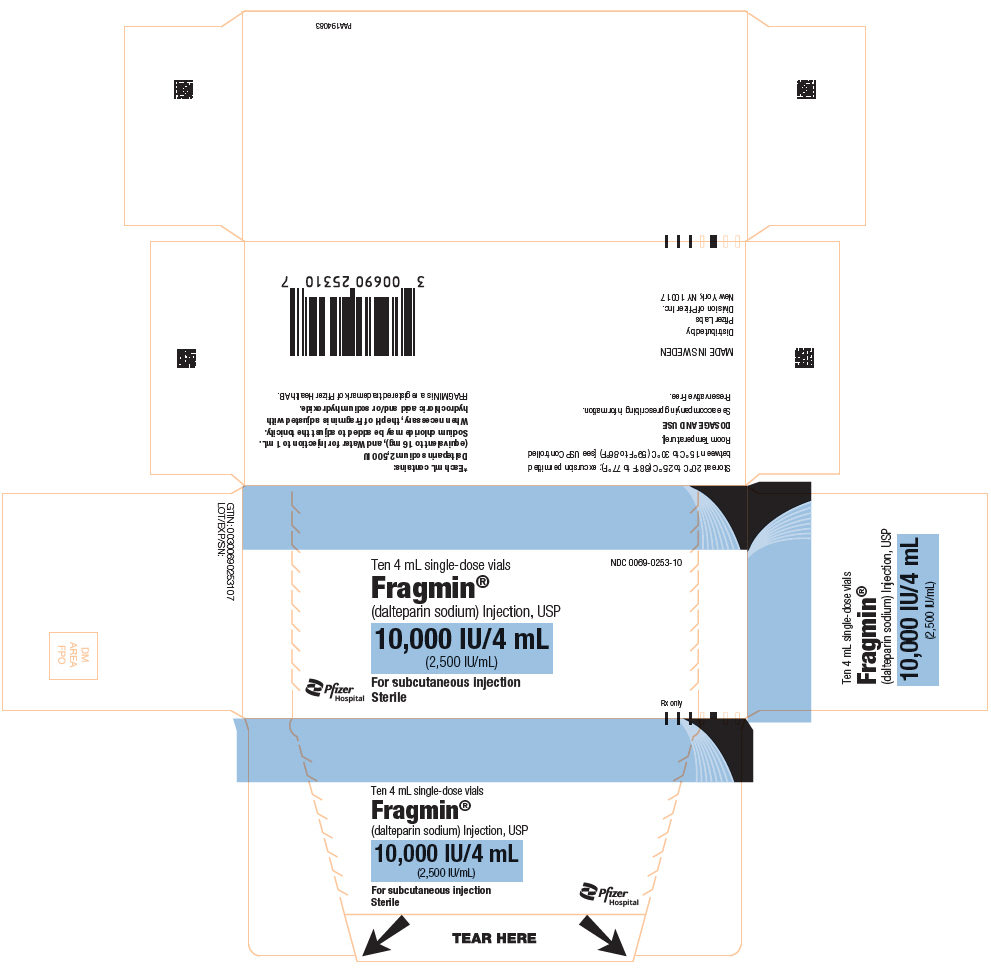 DRUG LABEL: Fragmin
NDC: 0069-0195 | Form: INJECTION
Manufacturer: Pfizer Laboratories Div Pfizer Inc
Category: prescription | Type: HUMAN PRESCRIPTION DRUG LABEL
Date: 20250930

ACTIVE INGREDIENTS: DALTEPARIN SODIUM 2500 [iU]/0.2 mL
INACTIVE INGREDIENTS: WATER; SODIUM CHLORIDE

HIGHLIGHTS OF PRESCRIBING INFORMATION

These highlights do not include all the information needed to use FRAGMIN safely and effectively. See full prescribing information for FRAGMIN.
FRAGMIN® (dalteparin sodium) injection, USP, for subcutaneous use
Initial U.S. Approval: 1994

RECENT MAJOR CHANGES

Indications and Usage, Treatment of Symptomatic Venous Thromboembolism (VTE) in Pediatric Patients (1.4) | 10/2024
Dosage and Administration, Treatment of Symptomatic Venous Thromboembolism (VTE) in Pediatric Patients (2.4) | 10/2024
Dosage and Administration, Dose Reductions for Thrombocytopenia in Adult Patients with Cancer and in Pediatric Patients with; Symptomatic VTE (2.5) | 10/2024

WARNING: SPINAL/EPIDURAL HEMATOMAS

See full prescribing information for complete boxed warning.

Epidural or spinal hematomas may occur in patients who are anticoagulated with low molecular weight heparins (LMWH) or heparinoids and are receiving neuraxial anesthesia or undergoing spinal puncture. These hematomas may result in long-term or permanent paralysis. Consider these risks when scheduling patients for spinal procedures. Factors that can increase the risk of developing epidural or spinal hematomas in these patients include:

- Use of indwelling epidural catheters
- Concomitant use of other drugs that affect hemostasis, such as non-steroidal anti-inflammatory drugs (NSAIDs), platelet inhibitors, other anticoagulants.
- A history of traumatic or repeated epidural or spinal punctures
- A history of spinal deformity or spinal surgery
- Optimal timing between the administration of FRAGMIN and neuraxial procedures is not known

Monitor patients frequently for signs and symptoms of neurological impairment. If neurological compromise is noted, urgent treatment is necessary.

Consider the benefits and risks before neuraxial intervention in patients anticoagulated or to be anticoagulated for thromboprophylaxis (5.1, 7).

1 INDICATIONS AND USAGE

FRAGMIN is a low molecular weight heparin (LMWH) indicated for

- Prophylaxis of ischemic complications of unstable angina and non-Q-wave myocardial infarction (1.1)
- Prophylaxis of deep vein thrombosis (DVT) in abdominal surgery, hip replacement surgery or medical patients with severely restricted mobility during acute illness (1.2)
- Extended treatment of symptomatic venous thromboembolism (VTE) to reduce the recurrence in adult patients with cancer. In these patients, the FRAGMIN therapy begins with the initial VTE treatment and continues for six months (1.3)
- Treatment of symptomatic venous thromboembolism (VTE) to reduce the recurrence in pediatric patients from birth (gestational age at least 35 weeks) (1.4)
- Limitations of Use
  FRAGMIN is not indicated for the acute treatment of VTE (1.5)

2 DOSAGE AND ADMINISTRATION

Indication | Dosing Regimen
Unstable angina and non-Q-wave MI | 120 units/kg subcutaneous every 12 hours (with aspirin) (2.1)
DVT prophylaxis in abdominal surgery | 2,500 units subcutaneous once daily or 5,000 units subcutaneous once daily or 2,500 units subcutaneous followed by 2,500 units subcutaneous 12 hours later and then 5,000 units subcutaneous once daily (2.2)
DVT prophylaxis in hip replacement surgery | Postoperative start – 2,500 units subcutaneous 4 hours to 8 hours after surgery, then 5,000 units subcutaneous once daily, or Preoperative start – day of surgery 2,500 units subcutaneous 2 hours before surgery followed by 2,500 units subcutaneous 4 hours to 8 hours after surgery, then 5,000 units subcutaneous once daily (2.2) Preoperative start – Evening Before Surgery 5,000 units subcutaneous followed by 5,000 units subcutaneous 4 hours to 8 hours after surgery (2.2)
DVT prophylaxis in medical patients | 5,000 units subcutaneous once daily (2.2)
Extended treatment of VTE in adult patients with cancer | Month 1: 200 units/kg subcutaneous once daily (2.3) Months 2 to 6: 150 units/kg subcutaneous once daily (2.3)
Treatment of VTE in pediatric patients (see Table 5) (2.4) | Age Group | Starting Dose
Treatment of VTE in pediatric patients (see Table 5) (2.4) | Birth (gestational age; at least 35 weeks) to less than 2 Years | 150 units/kg twice daily
Treatment of VTE in pediatric patients (see Table 5) (2.4) | 2 Years to less than 8 Years | 125 units/kg twice daily
Treatment of VTE in pediatric patients (see Table 5) (2.4) | 8 Years to less than 17 Years | 100 units/kg twice daily

Do not use as intramuscular injection. FRAGMIN should not be mixed with other injections or infusions (2.7)

3 DOSAGE FORMS AND STRENGTHS

- Injection: 2,500 units/ 0.2 mL, 5,000 units/ 0.2 mL, 7,500 units/ 0.3 mL, 12,500 units/ 0.5 mL, 15,000 units/ 0.6 mL, and 18,000 units/ 0.72 mL single-dose prefilled syringes (3)
- Injection: 10,000 units/mL single-dose graduated syringes (3)
- Injection: 95,000 units/ 3.8 mL (25,000 units/mL) multiple-dose vials (3)
- Injection: 10,000 units/ 4 mL (2,500 units/mL) single-dose vials (3)

4 CONTRAINDICATIONS

- Active major bleeding (4)
- History of heparin induced thrombocytopenia or heparin induced thrombocytopenia with thrombosis (4)
- Hypersensitivity to dalteparin sodium (4, 6.1)
- In patients undergoing Epidural/Neuraxial anesthesia, do not administer FRAGMIN (5.1)
  - As a treatment for unstable angina and non-Q-wave MI
  - For prolonged VTE prophylaxis (4)
- Hypersensitivity to heparin or pork products (4)

5 WARNINGS AND PRECAUTIONS

- Hemorrhage: Use caution in conditions with increased risk of hemorrhage (5.1)
- Thrombocytopenia: Monitor thrombocytopenia of any degree closely (5.2)
- Benzyl Alcohol Preservative: Do not use multiple-dose formulations in neonates and infants as they contain benzyl alcohol (5.3)
- Laboratory Tests: Periodic blood counts recommended (5.4)

6 ADVERSE REACTIONS

Most common adverse reactions (>1%) are: bleeding (including hemorrhage), thrombocytopenia (Type I), hematoma at the injection site, pain at the injection site, transient elevation of transaminases (6)

To report SUSPECTED ADVERSE REACTIONS, contact Pfizer Inc. at 1-800-438-1985 or FDA at 1-800-FDA-1088 or www.fda.gov/medwatch.

7 DRUG INTERACTIONS

The use of FRAGMIN in patients receiving oral anticoagulants, platelet inhibitors, and thrombolytic agents may increase the risk of bleeding (7)

FULL PRESCRIBING INFORMATION

WARNING: SPINAL/EPIDURAL HEMATOMAS

Epidural or spinal hematomas may occur in patients who are anticoagulated with low molecular weight heparins (LMWH) or heparinoids and are receiving neuraxial anesthesia or undergoing spinal puncture. These hematomas may result in long-term or permanent paralysis. Consider these risks when scheduling patients for spinal procedures. Factors that can increase the risk of developing epidural or spinal hematomas in these patients include:

- Use of indwelling epidural catheters
- Concomitant use of other drugs that affect hemostasis, such as non-steroidal anti-inflammatory drugs (NSAIDs), platelet inhibitors, other anticoagulants.
- A history of traumatic or repeated epidural or spinal punctures
- A history of spinal deformity or spinal surgery
- Optimal timing between the administration of FRAGMIN and neuraxial procedures is not known

Monitor patients frequently for signs and symptoms of neurological impairment. If neurological compromise is noted, urgent treatment is necessary.

Consider the benefits and risks before neuraxial intervention in patients anticoagulated or to be anticoagulated for thromboprophylaxis [see Warnings and Precautions (5.1) and Drug Interactions (7)].

1 INDICATIONS AND USAGE

1.1 Prophylaxis of Ischemic Complications in Unstable Angina and Non-Q-Wave Myocardial Infarction

FRAGMIN Injection is indicated for the prophylaxis of ischemic complications in unstable angina and non-Q-wave myocardial infarction, when concurrently administered with aspirin therapy [see Clinical Studies (14.1)].

1.2 Prophylaxis of Deep Vein Thrombosis

FRAGMIN is indicated for the prophylaxis of deep vein thrombosis (DVT), which may lead to pulmonary embolism (PE):

- In patients undergoing hip replacement surgery [see Clinical Studies (14.2)];
- In patients undergoing abdominal surgery who are at risk for thromboembolic complications [see Clinical Studies (14.3)];
- In medical patients who are at risk for thromboembolic complications due to severely restricted mobility during acute illness [see Clinical Studies (14.4)].

1.3 Extended Treatment of Symptomatic Venous Thromboembolism (VTE) in Adult Patients with Cancer

FRAGMIN is indicated for the extended treatment of symptomatic venous thromboembolism (VTE) (proximal DVT and/or PE), to reduce the recurrence of VTE in adult patients with cancer. In these patients, the FRAGMIN therapy begins with the initial VTE treatment and continues for six months [see Clinical Studies (14.5)].

1.4 Treatment of Symptomatic Venous Thromboembolism (VTE) in Pediatric Patients

FRAGMIN is indicated for the treatment of symptomatic venous thromboembolism (VTE) to reduce the recurrence of VTE in pediatric patients from birth (gestational age at least 35 weeks).

1.5 Limitations of Use

FRAGMIN is not indicated for the acute treatment of VTE.

2 DOSAGE AND ADMINISTRATION

2.1 Recommended Dosage for Prophylaxis of Ischemic Complications in Unstable Angina and Non-Q-Wave Myocardial Infarction

In patients with unstable angina or non-Q-wave myocardial infarction, the recommended dose of FRAGMIN Injection is 120 units/kg of body weight, but not more than 10,000 units, subcutaneously every 12 hours with concurrent oral aspirin (75 mg to 165 mg once daily) therapy. Treatment should be continued until the patient is clinically stabilized. The usual duration of administration is 5 days to 8 days. Concurrent aspirin therapy is recommended except when contraindicated.

Table 1 lists the volume of FRAGMIN in mL (based on the 3.8 mL multiple-dose vial 25,000 units/mL) and quantity of FRAGMIN in units, to be administered for a range of patient weights.

Table 1
Quantity and Volume of FRAGMIN to be Administered by Patient Weight
Patient weight (kg) | <50 kg | 50 kg to 59 kg | 60 kg to 69 kg | 70 kg to 79 kg | 80 kg to 89 kg | ≥90 kg
Quantity of FRAGMIN (units) | 5,500 units | 6,500 units | 7,500 units | 9,000 units | 10,000 units | 10,000 units
Volume of FRAGMIN (mL) 95,000 units / 3.8 mL | 0.22 mL | 0.26 mL | 0.3 mL | 0.36 mL | 0.4 mL | 0.4 mL

2.2 Prophylaxis of Deep Vein Thrombosis

Prophylaxis of VTE Following Hip Replacement Surgery: Table 2 presents the dosing options for patients undergoing hip replacement surgery. The usual duration of administration is 5 days to 10 days after surgery; up to 14 days of treatment with FRAGMIN have been well tolerated in clinical trials.

Table 2
Dosing Options for Patients Undergoing Hip Replacement Surgery
Timing of First Dose of FRAGMIN | Dose of FRAGMIN to be Given Subcutaneously
Timing of First Dose of FRAGMIN | 10 Hours to 14 Hours Before Surgery | Within 2 Hours Before Surgery | 4 Hours to 8 Hours After Surgery [Or later, if hemostasis has not been achieved.] | Postoperative Period [Up to 14 days of treatment was well tolerated in controlled clinical trials, where the usual duration of treatment was 5 days to 10 days postoperatively.]
Postoperative Start | --- | --- | 2,500 units [Allow a minimum of 6 hours between this dose and the dose to be given on Postoperative Day 1. Adjust the timing of the dose on Postoperative Day 1 accordingly.] | 5,000 units once daily
Preoperative Start - Day of Surgery | --- | 2,500 units | 2,500 units | 5,000 units once daily
Preoperative Start - Evening Before Surgery [Allow approximately 24 hours between doses.] | 5,000 units | --- | 5,000 units | 5,000 units once daily

Abdominal Surgery: In patients undergoing abdominal surgery with a risk of thromboembolic complications, the recommended dose of FRAGMIN is 2,500 units administered by subcutaneous injection once daily, starting 1 hour to 2 hours prior to surgery and repeated once daily postoperatively. The usual duration of administration is 5 days to 10 days.

In patients undergoing abdominal surgery associated with a high risk of thromboembolic complications, such as malignant disorder, the recommended dose of FRAGMIN is 5,000 units subcutaneously the evening before surgery, then once daily postoperatively. The usual duration of administration is 5 days to 10 days. Alternatively, in patients with malignancy, 2,500 units of FRAGMIN can be administered subcutaneously 1 hour to 2 hours before surgery followed by 2,500 units subcutaneously 12 hours later, and then 5,000 units once daily postoperatively. The usual duration of administration is 5 days to 10 days.

Medical Patients During Acute Illness: In medical patients with severely restricted mobility during acute illness, the recommended dose of FRAGMIN is 5,000 units administered by subcutaneous injection once daily. In clinical trials, the usual duration of administration was 12 days to 14 days.

2.3 Extended Treatment of Symptomatic Venous Thromboembolism (VTE) in Adult Patients with Cancer

In adult patients with cancer and symptomatic VTE, the recommended dosing of FRAGMIN is as follows: for the first 30 days of treatment administer FRAGMIN 200 units/kg total body weight subcutaneously once daily. The total daily dose should not exceed 18,000 units. Table 3 lists the dose of FRAGMIN to be administered once daily during the first month for a range of patient weights.

Month 1

Table 3
Dose of FRAGMIN to be Administered Subcutaneously by Patient Weight during the First Month
Body Weight (kg) | FRAGMIN Dose (units) (prefilled syringe) once daily
≤56 kg | 10,000 units
57 kg to 68 kg | 12,500 units
69 kg to 82 kg | 15,000 units
83 kg to 98 kg | 18,000 units
≥99 kg | 18,000 units

Months 2 to 6

Administer FRAGMIN at a dose of approximately 150 units/kg, subcutaneously once daily during Months 2 through 6. The total daily dose should not exceed 18,000 units. Table 4 lists the dose of FRAGMIN to be administered once daily for a range of patient weights during months 2 to 6.

Table 4
Dose of FRAGMIN to be Administered Subcutaneously by Patient Weight during Months 2 to 6
Body Weight (kg) | FRAGMIN Dose (units) (prefilled syringe) once daily
≤56 kg | 7,500 units
57 kg to 68 kg | 10,000 units
69 kg to 82 kg | 12,500 units
83 kg to 98 kg | 15,000 units
≥99 kg | 18,000 units

Safety and efficacy beyond six months have not been evaluated in patients with cancer and acute symptomatic VTE [see Warnings and Precaution (5) and Adverse Reactions (6.1)].

2.4 Treatment of Symptomatic Venous Thromboembolism (VTE) in Pediatric Patients

The recommended starting dose according to pediatric age is provided in Table 5.

Table 5
Starting Doses for Pediatric Patients with Symptomatic VTE
Age Group | Starting Dose
Birth (gestational age at least 35 weeks) to less than 2 Years | 150 units/kg twice daily
2 Years to less than 8 Years | 125 units/kg twice daily
8 Years to less than 17 Years | 100 units/kg twice daily

After initiation of FRAGMIN, measure anti-Xa level prior to the 4th dose. Samples for anti-Xa level should be drawn 4 hours after administration of FRAGMIN. Adjust doses in increments of 25 units/kg to achieve target anti-Xa level between 0.5 units/mL and 1 unit/mL. Individualize the maintenance dose of FRAGMIN based on the dose that achieves target anti-Xa level collected 4 hours after administration of FRAGMIN. Monitor anti-Xa level periodically in pediatric patients to maintain anti-Xa level between 0.5 units/mL and 1 unit/mL [see Clinical Pharmacology (12.3) and Clinical Studies (14.5)].

The 3.8 mL multiple-dose vials of FRAGMIN contain 14 mg/mL of benzyl alcohol [see Warnings and Precautions (5.3)].

Whenever possible, administer benzyl alcohol-free formulations (prefilled syringes) in pediatric patients [see Warnings and Precautions (5.3) and Use in Specific Populations (8.4)].

The 10,000 units/4 mL (2,500 units/mL) single-dose vials are preservative-free. For treatment of neonates, use this vial presentation.

2.5 Dose Reductions for Thrombocytopenia in Adult Patients with Cancer and in Pediatric Patients with Symptomatic VTE

Dose reductions recommended in patients receiving FRAGMIN who experience thrombocytopenia are presented below in Table 6.

Table 6
 | Platelet Count less than or equal to 50,000/mm^3 | Platelet Count greater than 50,000/mm^3 up to 100,000/mm^3
Adults | Discontinue FRAGMIN until platelet count recovers to above 50,000/mm^3. | Reduce the daily dose of FRAGMIN by 2,500 units until the platelet count recovers to greater or equal to 100,000/mm^3.
Children from birth (gestational age at least 35 weeks) to less than 17 Years | Discontinue FRAGMIN until platelet count recovers to above 50,000/mm^3. | Reduce the daily dose of FRAGMIN by 50% until the platelet count recovers to greater or equal to 100,000/mm^3.

2.6 Dose Reductions for Renal Insufficiency in Extended Treatment of Acute Symptomatic VTE in Adult Patients with Cancer

In patients with severely impaired renal function (CrCl <30 mL/min), monitor anti-Xa levels to determine the appropriate FRAGMIN dose. Target anti-Xa range is 0.5 units/mL to 1.5 units/mL. When monitoring anti-Xa in these patients, perform sampling 4 hours to 6 hours after FRAGMIN dosing and only after the patient has received 3 to 4 doses [see Clinical Pharmacology (12.3)].

2.7 Administration

Latex Allergy: Persons with latex allergies should not handle the FRAGMIN prefilled syringe because the needle shield may contain natural rubber latex which may cause allergic reactions.

FRAGMIN is administered by subcutaneous injection. It must not be administered by intramuscular injection.

FRAGMIN Injection should not be mixed with other injections or infusions unless specific compatibility data are available that support such mixing.

Subcutaneous injection technique: Patients should be sitting or lying down and FRAGMIN administered by deep subcutaneous injection. FRAGMIN may be injected in a U-shape area around the navel, the upper outer side of the thigh or the upper outer quadrangle of the buttock. The injection site should be varied daily. When the area around the navel or the thigh is used, using the thumb and forefinger, you must lift up a fold of skin while giving the injection. The entire length of the needle should be inserted at a 45 to 90 degree angle.

Inspect FRAGMIN prefilled syringes and vials visually for particulate matter and discoloration prior to administration.

After first penetration of the rubber stopper, store the multiple-dose vials at room temperature for up to 2 weeks. Discard any unused solution after 2 weeks.

Instructions for using the prefilled single-dose syringes preassembled with needle guard devices

Fixed dose syringes: To ensure delivery of the full dose, do not expel the air bubble from the prefilled syringe before injection. Hold the syringe assembly by the open sides of the device. Remove the needle shield. Insert the needle into the injection area as instructed above. Depress the plunger of the syringe while holding the finger flange until the entire dose has been given. The needle guard will not be activated unless the entire dose has been given. Remove needle from the patient. Let go of the plunger and allow syringe to move up inside the device until the entire needle is guarded. Discard the syringe assembly in approved containers.

Graduated syringes: Hold the syringe assembly by the open sides of the device. Remove the needle shield. With the needle pointing up, prepare the syringe by expelling the air bubble and then continuing to push the plunger to the desired dose or volume, discarding the extra solution in an appropriate manner. Insert the needle into the injection area as instructed above. Depress the plunger of the syringe while holding the finger flange until the entire dose remaining in the syringe has been given. The needle guard will not be activated unless the entire dose has been given. Remove needle from the patient. Let go of the plunger and allow syringe to move up inside the device until the entire needle is guarded. Discard the syringe assembly in approved containers.

3 DOSAGE FORMS AND STRENGTHS

FRAGMIN (dalteparin sodium) injection is a sterile, aqueous, clear, colorless or straw-colored solution for injection, available in the following dosage forms and strengths:

- Injection: 2,500 units/ 0.2 mL, 5,000 units/ 0.2 mL, 7,500 units/ 0.3 mL, 12,500 units/ 0.5 mL, 15,000 units/ 0.6 mL, and 18,000 units/ 0.72 mL sterile, single-dose, prefilled syringes preassembled with a needle guard device.
- Injection: 10,000 units/mL sterile, single-dose, graduated syringes preassembled with a needle guard device.
- Injection: 95,000 units/ 3.8 mL (25,000 units/mL) sterile, multiple-dose vials.
- Injection: 10,000 units/ 4 mL (2,500 units/mL) sterile, single-dose vials.

4 CONTRAINDICATIONS

FRAGMIN is contraindicated in:

- Patients with active major bleeding.
- Patients with a history of heparin induced thrombocytopenia or heparin induced thrombocytopenia with thrombosis.
- Patients with prior hypersensitivity to dalteparin sodium (e.g., pruritis, rash, anaphylactic reactions) [see Adverse Reactions (6.1)].
- Patients undergoing Epidural/Neuraxial anesthesia, do not administer FRAGMIN [see Boxed Warning and Warnings and Precautions (5.1)];
  - As a treatment for unstable angina and non-Q-wave MI.
  - For prolonged VTE prophylaxis.
- Patients with prior hypersensitivity to heparin or pork products.

5 WARNINGS AND PRECAUTIONS

5.1 Risk of Hemorrhage including Spinal/Epidural Hematomas

Spinal or epidural hemorrhage and subsequent hematomas can occur with the associated use of low molecular weight heparins or heparinoids and neuraxial (spinal/epidural) anesthesia or spinal puncture. The risk of these events is higher with the use of post-operative indwelling epidural catheters, with the concomitant use of additional drugs affecting hemostasis such as NSAIDs, with traumatic or repeated epidural or spinal puncture, or in patients with a history of spinal surgery or spinal deformity [see Boxed Warning, Adverse Reactions (6.2), and Drug Interactions (7)].

To reduce the potential risk of bleeding associated with the concurrent use of FRAGMIN and epidural or spinal anesthesia/analgesia or spinal puncture, consider the pharmacokinetic profile of FRAGMIN [see Clinical Pharmacology (12.3)].

Placement or removal of an epidural catheter or lumbar puncture is best performed when the anticoagulant effect of FRAGMIN is low; however, the exact timing to reach a sufficiently low anticoagulant effect in each patient is not known. No additional hemostasis-altering medications should be administered due to the additive effects.

Patients on preoperative FRAGMIN thromboprophylaxis can be assumed to have altered coagulation. The first postoperative FRAGMIN thromboprophylaxis dose (2,500 units) should be administered 6 hours to 8 hours postoperatively. The second postoperative dose (2,500 units or 5,000 units) should occur no sooner than 24 hours after the first dose. Placement or removal of a catheter should be delayed for at least 12 hours after administration of 2,500 units once daily of FRAGMIN, at least 15 hours after the administration of 5,000 units once daily of FRAGMIN, and at least 24 hours after the administration of higher doses (200 units/kg once daily, 120 units/kg twice daily) of FRAGMIN. Anti-Xa levels are still detectable at these time points, and these delays are not a guarantee that neuraxial hematoma will be avoided.

Although a specific recommendation for timing of a subsequent FRAGMIN dose after catheter removal cannot be made, consider delaying this next dose for at least 4 hours, based on a benefit-risk assessment considering both the risk for thrombosis and the risk for bleeding in the context of the procedure and patient risk factors. For patients with creatinine clearance <30 mL/minute, additional considerations are necessary because elimination of FRAGMIN may be more prolonged; consider doubling the timing of removal of a catheter, at least 24 hours for the lower prescribed dose of FRAGMIN (2,500 units or 5,000 units once daily) and at least 48 hours for the higher dose (200 units/kg once daily, 120 units/kg twice daily) [see Clinical Pharmacology (12.3)].

Should the physician decide to administer anticoagulation in the context of epidural or spinal anesthesia/analgesia or lumbar puncture, frequent monitoring must be exercised to detect any signs and symptoms of neurological impairment such as midline back pain, sensory and motor deficits (numbness or weakness in lower limbs), bowel and/or bladder dysfunction. Instruct patients to report immediately if they experience any of the above signs or symptoms. If signs or symptoms of spinal hematoma are suspected, initiate urgent diagnosis and treatment including consideration for spinal cord decompression even though such treatment may not prevent or reverse neurological sequelae.

Use FRAGMIN with extreme caution in patients who have an increased risk of hemorrhage, such as those with severe uncontrolled hypertension, bacterial endocarditis, congenital or acquired bleeding disorders, active ulceration and angiodysplastic gastrointestinal disease, hemorrhagic stroke, or shortly after brain, spinal or ophthalmological surgery. FRAGMIN may enhance the risk of bleeding in patients with thrombocytopenia or platelet defects; severe liver or kidney insufficiency, hypertensive or diabetic retinopathy, and recent gastrointestinal bleeding. Bleeding can occur at any site during therapy with FRAGMIN.

5.2 Thrombocytopenia

Heparin-induced thrombocytopenia can occur with the administration of FRAGMIN. The incidence of this complication is unknown at present. In clinical practice, cases of thrombocytopenia with thrombosis, amputation and death have been observed [see Contraindications (4)]. Closely monitor thrombocytopenia of any degree.

In FRAGMIN clinical trials supporting non-cancer indications, platelet counts of <50,000/mm^3 occurred in <1% of patients.

In the clinical trial of adult patients with cancer and acute symptomatic VTE treated for up to 6 months in the FRAGMIN treatment arm, platelet counts of <100,000/mm^3 occurred in 13.6% of patients, including 6.5% who also had platelet counts less than 50,000/mm^3. In the same clinical trial, thrombocytopenia was reported as an adverse event in 10.9% of patients in the FRAGMIN arm and 8.1% of patients in the Oral Anti-Coagulant (OAC) arm. FRAGMIN dose was decreased or interrupted in patients whose platelet counts fell below 100,000/mm^3.

In the clinical trial of pediatric patients with or without cancer with acute symptomatic VTE treated for up to 3 months with FRAGMIN, platelet counts of <100,000/mm^3 occurred in 37% of patients, including 21% who also had platelet counts less than 50,000/mm^3. In the same clinical trial, thrombocytopenia was reported as an adverse reaction in 21% of patients. FRAGMIN dose was interrupted in patients whose platelet counts fell below 50,000/mm^3.

5.3 Risk of Serious Adverse Reactions in Neonates and Infants due to Benzyl Alcohol Preservative

Use preservative-free FRAGMIN in neonates and infants.

Serious and fatal adverse reactions including "gasping syndrome" can occur in neonates and low-birth weight infants treated with medications that contain the preservative benzyl alcohol. The "gasping syndrome" is characterized by central nervous system depression, metabolic acidosis, and gasping respirations. When prescribing FRAGMIN in infants, consider the combined daily metabolic load of benzyl alcohol from all sources including FRAGMIN multiple-dose vial (contains 14 mg of benzyl alcohol per mL) and other drugs containing benzyl alcohol. The minimum amount of benzyl alcohol at which serious adverse reactions may occur is not known [see Use in Specific Populations (8.4)]. Because benzyl alcohol may cross the placenta, use caution when administering FRAGMIN preserved with benzyl alcohol to pregnant women. If anticoagulation with FRAGMIN is needed during pregnancy, use preservative-free formulations where possible [see Use in Specific Populations (8.1)].

5.4 Laboratory Tests

Periodic routine complete blood counts, including platelet count, blood chemistry, and stool occult blood tests are recommended during the course of treatment with FRAGMIN. When administered at recommended prophylaxis doses, routine coagulation tests such as Prothrombin Time (PT) and Activated Partial Thromboplastin Time (APTT) are relatively insensitive measures of FRAGMIN activity and, therefore, unsuitable for monitoring the anticoagulant effect of FRAGMIN. Monitor anti-Xa level periodically in pediatric patients. Anti-Xa may be used to monitor the anticoagulant effect of FRAGMIN, such as in patients with severe renal impairment or if abnormal coagulation parameters or bleeding occurs during FRAGMIN therapy.

6 ADVERSE REACTIONS

The following clinically significant adverse reactions are described in more detail in other sections of the prescribing information.

- Risk of Hemorrhage including Spinal/Epidural Hematomas [see Warnings and Precautions (5.1)]
- Thrombocytopenia [see Warnings and Precautions (5.2)]
- Benzyl Alcohol Preservative Risk to Premature Infants [see Warnings and Precautions (5.3)]

6.1 Clinical Trials Experience

Because clinical trials are conducted under widely varying conditions, adverse reaction rates observed in the clinical trials of a drug cannot be directly compared to rates in the clinical trials of another drug and may not accurately reflect the rates observed in practice.

Hemorrhage

The most commonly reported adverse reactions are hematoma at the injection site and hemorrhagic complications. The risk for bleeding varies with the indication and may increase with higher doses.

Unstable Angina and Non-Q-Wave Myocardial Infarction

Table 7 summarizes major bleeding reactions that occurred with FRAGMIN, heparin, and placebo in clinical trials of unstable angina and non-Q-wave myocardial infarction.

Table 7
Major Bleeding Reactions in Unstable Angina and Non-Q-Wave Myocardial Infarction
Indication | Dosing Regimen
Unstable Angina and Non-Q-Wave MI | FRAGMIN 120 units/kg/12 hours subcutaneous [Treatment was administered for 5 days to 8 days.] n (%) | Heparin [Heparin intravenous infusion for at least 48 hours, APTT 1.5 to 2 times control, then 12,500 units subcutaneously every 12 hours for 5 days to 8 days.] intravenous and subcutaneous n (%) | Placebo every 12 hours subcutaneous n (%)
Major Bleeding Reactions [Aspirin (75 mg to 165 mg per day) and beta blocker therapies were administered concurrently.] , [Bleeding reactions were considered major if: 1) accompanied by a decrease in hemoglobin of ≥2 g/dL in connection with clinical symptoms; 2) a transfusion was required; 3) bleeding led to interruption of treatment or death; or 4) intracranial bleeding.] | 15/1497 (1.0) | 7/731 (1.0) | 4/760 (0.5)

Hip Replacement Surgery

Table 8 summarizes: 1) all major bleeding reactions and, 2) other bleeding reactions possibly or probably related to treatment with FRAGMIN (preoperative dosing regimen), warfarin sodium, or heparin in two hip replacement surgery clinical trials.

Table 8
Bleeding Reactions Following Hip Replacement Surgery
Indication | FRAGMIN vs Warfarin Sodium |  | FRAGMIN vs Heparin
Indication | Dosing Regimen |  | Dosing Regimen
Hip Replacement Surgery | FRAGMIN [Includes three treated patients who did not undergo a surgical procedure.] 5,000 units once daily subcutaneous | Warfarin Sodium [Warfarin sodium dosage was adjusted to maintain a prothrombin time index of 1.4 to 1.5, corresponding to an International Normalized Ratio (INR) of approximately 2.5.] oral | FRAGMIN [Includes two treated patients who did not undergo a surgical procedure.] 5,000 units once daily subcutaneous | Heparin 5,000 units three times a day subcutaneous
Hip Replacement Surgery | n (%) | n (%) | n (%) | n (%)
Major Bleeding Reactions [A bleeding event was considered major if: 1) hemorrhage caused a significant clinical event, 2) it was associated with a hemoglobin decrease of ≥2 g/dL or transfusion of 2 or more units of blood products, 3) it resulted in reoperation due to bleeding, or 4) it involved retroperitoneal or intracranial hemorrhage.] | 7/274 (2.6) | 1/279 (0.4) | 0 | 3/69 (4.3)
Other Bleeding Reactions [Occurred at a rate of at least 2% in the group treated with FRAGMIN 5,000 units once daily.] Hematuria | 8/274 (2.9) | 5/279 (1.8) | 0 | 0
Wound Hematoma | 6/274 (2.2) | 0 | 0 | 0
Injection Site Hematoma | 3/274 (1.1) | NA | 2/69 (2.9) | 7/69 (10.1)

Six of the patients treated with FRAGMIN experienced seven major bleeding reactions. Two of the reactions were wound hematoma (one requiring reoperation), three were bleeding from the operative site, one was intraoperative bleeding due to vessel damage, and one was gastrointestinal bleeding.

In the third hip replacement surgery clinical trial, the incidence of major bleeding reactions was similar in all three treatment groups: 3.6% (18/496) for patients who started FRAGMIN before surgery; 2.5% (12/487) for patients who started FRAGMIN after surgery; and 3.1% (15/489) for patients treated with warfarin sodium.

Abdominal Surgery

Table 9 summarizes bleeding reactions that occurred in clinical trials which studied FRAGMIN 2,500 units and 5,000 units administered once daily to abdominal surgery patients.

Table 9
Bleeding Reactions Following Abdominal Surgery
Indication | FRAGMIN vs Placebo |  | FRAGMIN vs FRAGMIN
Indication | Dosing Regimen |  | Dosing Regimen
Abdominal Surgery | FRAGMIN 2,500 units once daily subcutaneous n (%) | Placebo once daily subcutaneous n (%) | FRAGMIN 2,500 units once daily subcutaneous n (%) | FRAGMIN 5,000 units once daily subcutaneous n (%)
Postoperative Transfusions | 14/182 (7.7) | 13/182 (7.1) | 89/1,025 (8.7) | 125/1,033 (12.1)
Wound Hematoma | 2/79 (2.5) | 2/77 (2.6) | 1/1,030 (0.1) | 4/1,039 (0.4)
Reoperation Due to Bleeding | 1/79 (1.3) | 1/78 (1.3) | 2/1,030 (0.2) | 13/1,038 (1.3)
Injection Site Hematoma | 8/172 (4.7) | 2/174 (1.1) | 36/1,026 (3.5) | 57/1,035 (5.5)

Table 9 Cont.
Bleeding Reactions Following Abdominal Surgery
Indication | FRAGMIN vs Heparin
Indication | Dosing Regimen
Abdominal Surgery | FRAGMIN 2,500 units once daily subcutaneous n (%) | Heparin 5,000 units twice daily subcutaneous n (%) | FRAGMIN 5,000 units once daily subcutaneous n (%) | Heparin 5,000 units twice daily subcutaneous n (%)
Postoperative Transfusions | 26/459 (5.7) | 36/454 (7.9) | 81/508 (15.9) | 63/498 (12.7)
Wound Hematoma | 16/467 (3.4) | 18/467 (3.9) | 12/508 (2.4) | 6/498 (1.2)
Reoperation Due to Bleeding | 2/392 (0.5) | 3/392 (0.8) | 4/508 (0.8) | 2/498 (0.4)
Injection Site Hematoma | 1/466 (0.2) | 5/464 (1.1) | 36/506 (7.1) | 47/493 (9.5)

In a trial comparing FRAGMIN 5,000 units once daily to FRAGMIN 2,500 units once daily in patients undergoing surgery for malignancy, the incidence of bleeding reactions was 4.6% and 3.6%, respectively (n.s.). In a trial comparing FRAGMIN 5,000 units once daily to heparin 5,000 units twice daily, in the malignancy subgroup the incidence of bleeding reactions was 3.2% and 2.7%, respectively for FRAGMIN and Heparin (n.s.).

Medical Patients with Severely Restricted Mobility During Acute Illness

Table 10 summarizes major bleeding reactions that occurred in a clinical trial of medical patients with severely restricted mobility during acute illness.

Table 10
Bleeding Reactions in Medical Patients with Severely Restricted Mobility During Acute Illness
Indication | Dosing Regimen
Medical Patients with Severely Restricted Mobility | FRAGMIN 5,000 units once daily subcutaneous n (%) | Placebo once daily subcutaneous n (%)
Major Bleeding Reactions [A bleeding event was considered major if: 1) it was accompanied by a decrease in hemoglobin of ≥2 g/dL in connection with clinical symptoms; 2) intraocular, spinal/epidural, intracranial, or retroperitoneal bleeding; 3) required transfusion of ≥2 units of blood products; 4) required significant medical or surgical intervention; or 5) led to death.] at Day 14 | 8/1,848 (0.4) | 0/1,833 (0)
Major Bleeding Reactions at Day 21 | 9/1,848 (0.5) | 3/1,833 (0.2)

Three of the major bleeding reactions that occurred by Day 21 were fatal, all due to gastrointestinal hemorrhage (two patients in the group treated with FRAGMIN and one in the group receiving placebo).

Adult Patients with Cancer and Acute Symptomatic VTE

Table 11 summarizes the number of patients with bleeding reactions that occurred in the clinical trial of adult patients with cancer and acute symptomatic VTE. A bleeding event was considered major if it: 1) was accompanied by a decrease in hemoglobin of ≥2 g/dL in connection with clinical symptoms; 2) occurred at a critical site (intraocular, spinal/epidural, intracranial, retroperitoneal, or pericardial bleeding); 3) required transfusion of ≥2 units of blood products; or 4) led to death. Minor bleeding was classified as clinically overt bleeding that did not meet criteria for major bleeding.

At the end of the six-month study, a total of 46 (13.6%) patients in the FRAGMIN arm and 62 (18.5%) patients in the OAC arm experienced any bleeding event. One bleeding event (hemoptysis in a patient in the FRAGMIN arm at Day 71) was fatal.

Table 11
Bleeding Reactions (Major and Any) (As treated population) [Patients with multiple bleeding episodes within any time interval were counted only once in that interval. However, patients with multiple bleeding episodes that occurred at different time intervals were counted once in each interval in which the event occurred.]
Study period | FRAGMIN; 200 units/kg (max. 18,000 units) subcutaneous once daily x 1 month, then 150 units/kg (max. 18,000 units) subcutaneous once daily x 5 months |  |  | OAC; FRAGMIN 200 units/kg (max 18,000 units) subcutaneous once daily x 5 to 7 days and OAC for 6 months (target INR 2 to 3)
Study period | Number at risk | Patients with Major Bleeding; n (%) | Patients with Any Bleeding; n (%) | Number at risk | Patients with Major Bleeding; n (%) | Patients with Any Bleeding; n (%)
Total during study | 338 | 19 (5.6) | 46 (13.6) | 335 | 12 (3.6) | 62 (18.5)
Week 1 | 338 | 4 (1.2) | 15 (4.4) | 335 | 4 (1.2) | 12 (3.6)
Weeks 2 to 4 | 332 | 9 (2.7) | 17 (5.1) | 321 | 1 (0.3) | 12 (3.7)
Weeks 5 to 28 | 297 | 9 (3.0) | 26 (8.8) | 267 | 8 (3) | 40 (15)

Elevations of Serum Transaminases

In FRAGMIN clinical trials supporting non-cancer indications, where hepatic transaminases were measured, asymptomatic increases in transaminase levels (SGOT/AST and SGPT/ALT) greater than three times the upper limit of normal of the laboratory reference range were seen in 4.7% and 4.2%, respectively, of patients during treatment with FRAGMIN.

In the FRAGMIN clinical trial of patients with cancer and acute symptomatic venous thromboembolism treated with FRAGMIN for up to 6 months, asymptomatic increases in transaminase levels, AST and ALT, greater than three times the upper limit of normal of the laboratory reference range were reported in 8.9% and 9.5% of patients, respectively. The frequencies of Grades 3 and 4 increases in AST and ALT, as classified by the National Cancer Institute, Common Toxicity Criteria (NCI-CTC) Scoring System, were 3% and 3.8%, respectively. Grades 2, 3 & 4 combined have been reported in 12% and 14% of patients, respectively.

Other

Allergic Reactions: Allergic reactions (i.e., pruritus, rash, fever, injection site reaction, bullous eruption) have occurred. Cases of anaphylactoid reactions have been reported.

Local Reactions: Pain at the injection site was reported in 4.5% of patients treated with FRAGMIN 5,000 units once daily vs 11.8% of patients treated with heparin 5,000 units twice daily in the abdominal surgery trials. In the hip replacement trials, pain at injection site was reported in 12% of patients treated with FRAGMIN 5,000 units once daily vs 13% of patients treated with heparin 5,000 units three times a day.

Pediatric Patients with Symptomatic VTE

The data below reflect exposure to FRAGMIN from two studies in pediatric patients from newborn to less than 18 years of age with or without cancer and symptomatic VTE (n = 50). Patients were started on FRAGMIN using age and weight-based dosing via subcutaneous injection twice daily. Anti-Xa levels were measured prior to the 4th dose and then periodically to determine whether dose adjustments were required, using 25 units/kg increments, to achieve a target anti-Xa level of 0.5 units/mL to 1.0 units/mL. The median time on treatment with FRAGMIN was 86 days (range 2 days to 170 days).

In pediatric patients with symptomatic VTE, the most common (greater than 10%) adverse reactions were injection site bruising (30%), contusion (12%), and epistaxis (10%).

Major bleeding was defined as any fatal bleeding, clinically overt bleeding with a decrease in hemoglobin of ≥2g/dL in 24 hours, overt bleeding deemed by the attending physician to be unrelated to the subject's underlying condition and accompanied by blood product administration, overt bleeding that was retroperitoneal, intracranial, intraspinal, intraocular, or intraarticular, or overt bleeding deemed by the attending physician to necessitate permanent discontinuation of trial medication. Major bleeding (intestinal hematoma) occurred in one patient (2%). Discontinuation due to adverse reactions occurred in 12% of patients, most often due to thrombocytopenia (4%).

Neonatal Patients

No controlled clinical trials have been conducted with FRAGMIN in neonatal patients with VTE; however, data are available from a non‑interventional retrospective medical chart review study of 16 neonates with VTE in the UK who were admitted to hospital between January 2010 and December 2021 and were treated with FRAGMIN. The mean (±SD) duration of dalteparin treatment was 62±30 days. For these 16 neonatal patients, the mean (±SD) daily dose of dalteparin at initiation was 365±196 units/kg (median:309 units/kg). The mean (±SD) daily dose of dalteparin including dose at initiation and dose changes was 575±320 units/kg (median: 450 units/kg). After the initial dose, all patients required one or more dose changes; 15 of 16 patients required dose increases due to anti-Xa level being initially below the target range of 0.5 units/mL to 1 units/mL.

The safety profile in neonates was similar to other pediatric patients.

6.2 Postmarketing Experience

The following adverse reactions have been identified during post-approval use of FRAGMIN. Because these reactions are reported voluntarily from a population of uncertain size, it is not always possible to reliably estimate their frequency or establish a causal relationship to drug exposure.

Since first international market introduction in 1985, there have been more than 15 reports of epidural or spinal hematoma formation with concurrent use of FRAGMIN and spinal/epidural anesthesia or spinal puncture. The majority of patients had postoperative indwelling epidural catheters placed for analgesia or received additional drugs affecting hemostasis. In some cases, the hematoma resulted in long-term or permanent paralysis (partial or complete) [see Boxed Warning].

Musculoskeletal system: Osteoporosis

Skin or subcutaneous tissues disorders: Skin necrosis, cases of alopecia reported that improved on drug discontinuation

Metabolism and nutrition disorders: Hyperkalemia

7 DRUG INTERACTIONS

The use of FRAGMIN in patients receiving oral anticoagulants, platelet inhibitors, and thrombolytic agents may increase the risk of bleeding [see Warnings and Precautions (5)].

8 USE IN SPECIFIC POPULATIONS

8.1 Pregnancy

Risk Summary

Available data from published literature and postmarketing reports have not reported a clear association with FRAGMIN and adverse developmental outcomes. There are risks to the mother associated with untreated VTE in pregnancy, and a potential for adverse effects on the preterm infant when FRAGMIN is used in pregnancy (see Clinical Considerations). In animal reproduction studies, there was no evidence of embryo-fetal toxicity or teratogenicity when dalteparin sodium was administered to pregnant rats and rabbits during organogenesis at doses 2 to 4 times (rats) and 4 times (rabbits) the human dose of 100 units/kg dalteparin based on the body surface area (see Data). Because animal reproduction studies are not always predictive of human response, FRAGMIN should be used during pregnancy only if clearly needed.

The estimated background risk of major birth defects and miscarriage for the indicated population is unknown. All pregnancies have a background risk of birth defect, loss, or other adverse outcomes. In the U.S. general population, the estimated background risk of major birth defects and miscarriage in clinically recognized pregnancies is 2% to 4% and 15% to 20%, respectively.

Clinical Considerations

Disease-Associated Maternal and/or Embryo/Fetal Risk

Published data describe that women with a previous history of VTE in pregnancy are at higher risk for recurrence during subsequent pregnancies compared to those with no risk factor for VTE (4.5% versus 2.7% respectively, relative risk 1.7, 95% CI: 1.0–2.8).

Fetal/Neonatal Adverse Reactions

Cases of "gasping syndrome" have occurred in premature infants when large amounts of benzyl alcohol have been administered (99 mg/kg/day to 404 mg/kg/day). The 3.8 mL multiple-dose vials of FRAGMIN contain 14 mg/mL of benzyl alcohol [see Warnings and Precautions (5.3)].

Data

Animal Data

In reproductive and developmental toxicity studies, pregnant rats and rabbits received dalteparin sodium during organogenesis at intravenous doses up to 2,400 units/kg (14,160 units/m^2) (rats) and 4,800 units/kg (40,800 units/m^2) (rabbits). These exposures were 2 to 4 times (rats) and 4 times (rabbits) the human dose of 100 units/kg dalteparin based on the body surface area. These studies revealed no evidence of teratogenicity or embryo-fetal toxicity.

8.2 Lactation

Risk Summary

Limited published data indicate that dalteparin is present in human milk in small amounts (see Data). No adverse effects on the breastfed infant have been reported. There are no data on the effects of the drug on milk production. Oral absorption of dalteparin is expected to be low, but the clinical implications, if any, of this small amount of anticoagulant activity on a breastfed infant are unknown. The developmental and health benefits of breastfeeding should be considered along with the mother's clinical need for FRAGMIN and any potential adverse effects on the breastfed child from FRAGMIN or from the underlying maternal condition.

Data

A study evaluated samples of maternal blood and breast milk in 15 lactating women receiving prophylactic doses of dalteparin in the immediate postpartum period (days 4 to 8 after Cesarean-section). The samples were collected before and 3 hours to 4 hours after daily injections of 2500 units dalteparin. Small amounts of anti-Xa activity (range <0.005 to 0.037 units/mL) in breast milk were detected in 11 of the 15 women. Because this study evaluated colostrum or transitional milk at a single timepoint during the 24 hours dosing interval, the clinical relevance of this data is unclear in regard to passage of drug into mature milk and the quantification of drug exposure to the infant over the full dosing interval.

8.4 Pediatric Use

The safety and effectiveness of FRAGMIN for the treatment of symptomatic venous thromboembolism (VTE) in patients have been established in pediatric patients from birth (gestational age at least 35 weeks) to less than 17 years of age.

Use of FRAGMIN for this indication is supported by evidence from well-controlled studies in adults with additional pharmacokinetic, pharmacodynamic, efficacy, and safety data from two separate prospective studies in pediatric patients aged 1 month and older with symptomatic VTE, and a retrospective study in neonatal patients aged birth (gestational age at least 35 weeks) to 1 month with VTE [see Adverse Reactions (6.1), Clinical Pharmacology (12.3), and Clinical Studies (14.5]. The frequency, type and severity of adverse reactions observed were generally consistent with those observed in adults.

Use preservative-free FRAGMIN in neonates and infants.

Serious adverse reactions including fatal reactions and the “gasping syndrome” occurred in premature neonates and low-birth weight infants in the neonatal intensive care unit who received benzyl alcohol preserved medications. In these cases, benzyl alcohol dosages of 99 mg/kg/day to 234 mg/kg/day produced high levels of benzyl alcohol and its metabolites in the blood and urine (blood levels of benzyl alcohol were 0.61 mmol/L to 1.378 mmol/L). Additional adverse reactions included gradual neurological deterioration, seizures, intracranial hemorrhage, hematologic abnormalities, skin breakdown, hepatic and renal failure, hypotension, bradycardia, and cardiovascular collapse. Preterm, low-birth weight infants may be more likely to develop these reactions because they may be less able to metabolize benzyl alcohol.

When prescribing FRAGMIN multiple-dose vials in infants consider the combined daily metabolic load of benzyl alcohol from all sources including FRAGMIN multiple-dose vials (FRAGMIN contains 14 mg of benzyl alcohol per mL) and other drugs containing benzyl alcohol. The minimum amount of benzyl alcohol at which serious adverse reactions may occur is not known [see Warnings and Precautions (5.3)].

The long-term effects of treatment with FRAGMIN in pediatric patients, including effects on growth and bone metabolism, are unknown.

8.5 Geriatric Use

Of the total number of patients in clinical studies of FRAGMIN, 5,516 patients were 65 years of age or older and 2,237 were 75 or older. No overall differences in effectiveness were observed between these subjects and younger subjects. Some studies suggest that the risk of bleeding increases with age. Postmarketing surveillance and literature reports have not revealed additional differences in the safety of FRAGMIN between elderly and younger patients. Give careful attention to dosing intervals and concomitant medications (especially antiplatelet medications) in geriatric patients, particularly in those with low body weight (<45 kg) and those predisposed to decreased renal function [see Warnings and Precautions (5) and Clinical Pharmacology (12)].

10 OVERDOSAGE

An excessive dosage of FRAGMIN Injection may lead to hemorrhagic complications. These may generally be stopped by slow intravenous injection of protamine sulfate (1% solution), at a dose of 1 mg protamine for every 100 anti-Xa units of FRAGMIN given. If the APTT measured 2 hours to 4 hours after the first infusion remains prolonged, a second infusion of 0.5 mg protamine sulfate per 100 anti-Xa units of FRAGMIN may be administered. Even with these additional doses of protamine, the APTT may remain more prolonged than would usually be found following administration of unfractionated heparin. In all cases, the anti-Xa activity is never completely neutralized (maximum about 60% to 75%).

Take particular care to avoid overdosage with protamine sulfate. Administration of protamine sulfate can cause severe hypotensive and anaphylactoid reactions. Because fatal reactions, often resembling anaphylaxis, have been reported with protamine sulfate, give protamine sulfate only when resuscitation techniques and treatment for anaphylactic shock are readily available. For additional information, consult the labeling of Protamine Sulfate Injection, USP, products.

11 DESCRIPTION

FRAGMIN Injection (dalteparin sodium injection) is a sterile, low molecular weight heparin. It is available in single-dose, prefilled syringes preassembled with a needle guard device, and multiple-dose vials. With reference to the W.H.O. First International Low Molecular Weight Heparin Reference Standard, each syringe contains either 2,500 units, 5,000 units, 7,500 units, 10,000 units, 12,500 units, 15,000 units or 18,000 anti-Xa international units (units), equivalent to 16 mg, 32 mg, 48 mg, 64 mg, 80 mg, 96 mg or 115.2 mg dalteparin sodium, respectively. Each multiple-dose vial contains 25,000 anti-Xa units per 1 mL (equivalent to 160 mg dalteparin sodium), for a total of 95,000 anti-Xa units per vial. Each single-dose vial contains 2,500 anti-Xa units per 1 mL (equivalent to 16 mg dalteparin sodium) for a total of 10,000 anti-Xa units per vial.

Each prefilled syringe also contains Water for Injection and sodium chloride, when required, to maintain physiologic ionic strength. The prefilled syringes are preservative-free. Each multiple-dose vial also contains Water for Injection and 14 mg of benzyl alcohol per mL as a preservative. The pH of both formulations is 5.0 to 7.5. When necessary, the pH of FRAGMIN is adjusted with hydrochloric acid and/or sodium hydroxide [see Dosage and Administration (2.7) and How Supplied/Storage and Handling (16)].

Dalteparin sodium is produced through controlled nitrous acid depolymerization of sodium heparin from porcine intestinal mucosa followed by a chromatographic purification process. It is composed of strongly acidic sulfated polysaccharide chains (oligosaccharide, containing 2,5-anhydro-D-mannitol residues as end groups) with an average molecular weight of 5,000 and about 90% of the material within the range 2,000–9,000. The molecular weight distribution is:

 | <3000 daltons | 3.0–15%
 | 3,000 to 8,000 daltons | 65.0–78.0%
 | >8,000 daltons | 14.0–26.0%

Structural Formula

12 CLINICAL PHARMACOLOGY

12.1 Mechanism of Action

Dalteparin is a low molecular weight heparin with antithrombotic properties. It acts by enhancing the inhibition of Factor Xa and thrombin by antithrombin. In humans, dalteparin potentiates preferentially the inhibition of coagulation Factor Xa, while only slightly affecting the activated partial thromboplastin time (APTT).

12.2 Pharmacodynamics

Doses of FRAGMIN Injection of up to 10,000 anti-Xa units administered subcutaneously as a single dose or two 5,000 units doses 12 hours apart to healthy subjects did not produce a significant change in platelet aggregation, fibrinolysis, or global clotting tests such as prothrombin time (PT), thrombin time (TT) or APTT. Subcutaneous administration of doses of 5,000 units twice daily of FRAGMIN for seven consecutive days to patients undergoing abdominal surgery did not markedly affect APTT, Platelet Factor 4 (PF4), or lipoprotein lipase.

12.3 Pharmacokinetics

Adults

Mean peak levels of plasma anti-Xa activity following single subcutaneous doses of 2,500 units, 5,000 units and 10,000 units were 0.19 ± 0.04 units/mL, 0.41 ± 0.07 units/mL and 0.82 ± 0.10 units/mL, respectively, and were attained in about 4 hours in most subjects. Absolute bioavailability in healthy volunteers, measured as the anti-Xa activity, was 87 ± 6%. Increasing the dose from 2,500 units to 10,000 units resulted in an overall increase in anti-Xa AUC that was greater than proportional by about one-third.

Peak anti-Xa activity increased more or less linearly with dose over the same dose range. There appeared to be no appreciable accumulation of anti-Xa activity with twice-daily dosing of 100 units/kg subcutaneously for up to 7 days.

The volume of distribution for dalteparin anti-Xa activity was 40 mL/kg to 60 mL/kg. The mean plasma clearances of dalteparin anti-Xa activity in normal volunteers following single intravenous bolus doses of 30 and 120 anti-Xa units/kg were 24.6 ± 5.4 mL/hr/kg and 15.6 ± 2.4 mL/hr/kg, respectively. The corresponding mean disposition half-lives were 1.47 ± 0.3 hours and 2.5 ± 0.3 hours.

Following intravenous doses of 40 units/kg and 60 units/kg, mean terminal half-lives were 2.1 ± 0.3 hours and 2.3 ± 0.4 hours, respectively. Longer apparent terminal half-lives (3 hours to 5 hours) are observed following subcutaneous dosing, possibly due to delayed absorption. In patients with chronic renal insufficiency requiring hemodialysis, the mean terminal half-life of anti-Xa activity following a single intravenous dose of 5,000 units FRAGMIN was 5.7 ± 2.0 hours, i.e., considerably longer than values observed in healthy volunteers, therefore, greater accumulation can be expected in these patients.

Pediatric Patients

The pharmacokinetics of twice-daily subcutaneous dalteparin, measured as anti-Xa activity, was characterized in 89 pediatric patients with or without cancer from two clinical studies and 1 observational study. Dalteparin pharmacokinetics (PK) were described by a 1-compartment model with linear absorption and elimination and PK parameters are shown in Table 12. After correcting for the body weight, clearance (CL/F) decreased with increasing age, while volume of distribution at steady-state (Vd/F) remained similar. The mean elimination half-life increased with age.

Table 12
Pharmacokinetic Parameters of Dalteparin in Pediatric Population
Parameter | 3 Weeks to <8 Weeks | ≥8 Weeks to <2 Years | ≥2 Years to <8 Years | ≥8 Years to <12 Years | ≥12 Years to <20 Years
Median Age (range) (years) | 0.06 (0.04 – 0.14) | 0.5 (0.2 – 1.91) | 4.47 (2.01 – 7.6) | 9.62 (8.01 – 10.5) | 15.9 (12.0 – 19.5)
Derived Mean (SD) CL/F (mL/h/kg) | 55.8 (3.91) | 40.4 (8.49) | 26.7 (4.75) | 22.4 (3.40) | 18.8 (3.01)
Derived Mean (SD) Vd/F (mL/kg) | 181 (15.3) | 175 (55.3) | 160 (25.6) | 165 (27.3) | 171 (38.9)
Derived Mean (SD) t½β (h) | 2.25 (0.173) | 3.02 (0.688) | 4.27 (1.05) | 5.11 (0.509) | 6.28 (0.937)
Abbreviations: CL=clearance; F=absolute bioavailability; SD=standard deviation; t½β=elimination half-life; Vd=volume of distribution.

13 NONCLINICAL TOXICOLOGY

13.1 Carcinogenesis, Mutagenesis, Impairment of Fertility

Dalteparin sodium has not been tested for its carcinogenic potential in long-term animal studies. It was not mutagenic in the in vitro Ames Test, mouse lymphoma cell forward mutation test and human lymphocyte chromosomal aberration test and in the in vivo mouse micronucleus test. Dalteparin sodium at subcutaneous doses up to 1,200 units/kg (7,080 units/m^2) did not affect the fertility or reproductive performance of male and female rats.

14 CLINICAL STUDIES

14.1 Prophylaxis of Ischemic Complications in Unstable Angina and Non-Q-Wave Myocardial Infarction

In a double-blind, randomized, placebo-controlled clinical trial, patients who recently experienced unstable angina with EKG changes or non-Q-wave myocardial infarction (MI) were randomized to FRAGMIN Injection 120 units/kg or placebo every 12 hours subcutaneously. In this trial, unstable angina was defined to include only angina with EKG changes. All patients, except when contraindicated, were treated concurrently with aspirin (75 mg once daily) and beta blockers. Treatment was initiated within 72 hours of the event (the majority of patients received treatment within 24 hours) and continued for 5 days to 8 days. A total of 1,506 patients were enrolled and treated; 746 received FRAGMIN and 760 received placebo. The mean age of the study population was 68 years (range 40 years to 90 years) and the majority of patients were white (99.7%) and male (63.9%). The combined incidence of the endpoint of death or myocardial infarction was lower for FRAGMIN compared with placebo at 6 days after initiation of therapy. These results were observed in an analysis of all-randomized and all-treated patients. The combined incidence of death, MI, need for intravenous heparin or intravenous. nitroglycerin, and revascularization was also lower for FRAGMIN than for placebo (see Table 13).

Table 13
Efficacy of FRAGMIN in the Prophylaxis of Ischemic Complications in Unstable Angina and Non-Q-Wave Myocardial Infarction
Indication | Dosing Regimen
Indication | FRAGMIN 120 units/kg/every 12 hours subcutaneous n (%) | Placebo every 12 hours subcutaneous n (%)
All Treated Unstable Angina and Non-Q-Wave MI Patients | 746 | 760
Primary Endpoints - 6 day timepoint Death, MI | 13/741 (1.8) [p-value = 0.001] | 36/757 (4.8)
Secondary Endpoints - 6 day timepoint Death, MI, intravenous heparin, i.v. nitroglycerin, Revascularization | 59/739 (8) | 106/756 (14)

In a second randomized, controlled trial designed to evaluate long-term treatment with FRAGMIN (6 days to 45 days), data were also collected comparing 1 week (5 days to 8 days) treatment of FRAGMIN 120 units/kg every 12 hours subcutaneously with heparin at an APTT-adjusted dosage. All patients, except when contraindicated, were treated concurrently with aspirin (100 mg per day to 165 mg per day). Of the 1,499 patients enrolled, 1,482 patients were treated; 751 received FRAGMIN and 731 received heparin. The mean age of the study population was 64 years (range 25 years to 92 years) and the majority of patients were white (96.0%) and male (64.2%). The incidence of the combined endpoint of death, myocardial infarction, or recurrent angina during this 1-week treatment period (5 days to 8 days) was 9.3% for FRAGMIN and 7.6% for heparin (p = 0.323).

14.2 Prophylaxis of Deep Vein Thrombosis in Patients Following Hip Replacement Surgery

In an open-label randomized study, FRAGMIN 5,000 units administered once daily subcutaneously was compared with warfarin sodium, administered orally, in patients undergoing hip replacement surgery. Treatment with FRAGMIN was initiated with a 2,500 units dose subcutaneously within 2 hours before surgery, followed by a 2,500 units dose subcutaneously the evening of the day of surgery. Then, a dosing regimen of FRAGMIN 5,000 units subcutaneously once daily was initiated on the first postoperative day. The first dose of warfarin sodium was given the evening before surgery, then continued daily at a dose adjusted for INR 2 to 3. Treatment in both groups was then continued for 5 days to 9 days postoperatively. Of the 580 patients enrolled, 553 were treated and 550 underwent surgery. Of those who underwent surgery, 271 received FRAGMIN and 279 received warfarin sodium. The mean age of the study population was 63 years (range 20 years to 92 years) and the majority of patients were white (91.1%) and female (52.9%). The incidence of deep vein thrombosis (DVT), as determined by evaluable venography, was significantly lower for the group treated with FRAGMIN compared with patients treated with warfarin sodium (see Table 14).

Table 14
Efficacy of FRAGMIN in the Prophylaxis of Deep Vein Thrombosis Following Hip Replacement Surgery
Indication | Dosing Regimen
Indication | FRAGMIN 5,000 units once daily [The daily dose on the day of surgery was divided: 2,500 units was given 2 hours before surgery and again in the evening of the day of surgery.] subcutaneous n (%) | Warfarin Sodium once daily [Warfarin sodium dosage was adjusted to maintain a prothrombin time index of 1.4 to 1.5, corresponding to an International Normalized Ratio (INR) of approximately 2.5] oral n (%)
All Treated Hip Replacement Surgery Patients | 271 | 279
Treatment Failures in Evaluable Patients DVT, Total | 28/192 (14.6) [p-value = 0.006] | 49/190 (25.8)
Proximal DVT | 10/192 (5.2) [p-value = 0.185] | 16/190 (8.4)
PE | 2/271 (0.7) | 2/279 (0.7)

In a second single-center, double-blind study of patients undergoing hip replacement surgery, FRAGMIN 5,000 units once daily subcutaneously starting the evening before surgery, was compared with heparin 5,000 units subcutaneously three times a day, starting the morning of surgery. Treatment in both groups was continued for up to 9 days postoperatively. Of the 140 patients enrolled, 139 were treated and 136 underwent surgery. Of those who underwent surgery, 67 received FRAGMIN and 69 received heparin. The mean age of the study population was 69 years (range 42 years to 87 years) and the majority of patients were female (58.8%). In the intent-to-treat analysis, the incidence of proximal DVT was significantly lower for patients treated with FRAGMIN compared with patients treated with heparin (6/67 vs 18/69; p = 0.012). The incidence of pulmonary embolism detected by lung scan was also significantly lower in the group treated with FRAGMIN (9/67 vs 19/69; p = 0.032).

A third multi-center, double-blind, randomized study evaluated a postoperative dosing regimen of FRAGMIN for thromboprophylaxis following total hip replacement surgery. Patients received either FRAGMIN or warfarin sodium, randomized into one of three treatment groups. One group of patients received the first dose of FRAGMIN 2,500 units subcutaneous within 2 hours before surgery, followed by another dose of FRAGMIN 2,500 units subcutaneous at least 4 hours (6.6 ± 2.3 hours) after surgery. Another group received the first dose of FRAGMIN 2,500 units subcutaneous at least 4 hours (6.6 ± 2.4 hours) after surgery. Then, both of these groups began a dosing regimen of FRAGMIN 5,000 units once daily subcutaneous on postoperative day 1. The third group of patients received warfarin sodium the evening of the day of surgery, then continued daily at a dose adjusted to maintain INR 2 to 3. Treatment for all groups was continued for 4 days to 8 days postoperatively, after which time all patients underwent bilateral venography.

In the total enrolled study population of 1,501 patients, 1,472 patients were treated; 496 received FRAGMIN (first dose before surgery), 487 received FRAGMIN (first dose after surgery) and 489 received warfarin sodium. The mean age of the study population was 63 years (range 18 years to 91 years) and the majority of patients were white (94.4%) and female (51.8%).

Administration of the first dose of FRAGMIN after surgery was as effective in reducing the incidence of thromboembolic reactions as administration of the first dose of FRAGMIN before surgery (44/336 vs 37/338; p =0.448). Both dosing regimens of FRAGMIN were more effective than warfarin sodium in reducing the incidence of thromboembolic reactions following hip replacement surgery.

14.3 Prophylaxis of Deep Vein Thrombosis Following Abdominal Surgery in Patients at Risk for Thromboembolic Complications

Abdominal surgery patients at risk include those who are over 40 years of age, obese, undergoing surgery under general anesthesia lasting longer than 30 minutes, or who have additional risk factors such as malignancy or a history of deep vein thrombosis or pulmonary embolism.

FRAGMIN administered once daily subcutaneously beginning prior to surgery and continued for 5 days to 10 days after surgery, reduced the risk of DVT in patients at risk for thromboembolic complications in two double-blind, randomized, controlled clinical trials performed in patients undergoing major abdominal surgery. In the first study, a total of 204 patients were enrolled and treated; 102 received FRAGMIN and 102 received placebo. The mean age of the study population was 64 years (range 40 years to 98 years) and the majority of patients were female (54.9%). In the second study, a total of 391 patients were enrolled and treated; 195 received FRAGMIN and 196 received heparin. The mean age of the study population was 59 years (range 30 years to 88 years) and the majority of patients were female (51.9%). FRAGMIN 2,500 units were superior to placebo and similar to heparin in reducing the risk of DVT (see Tables 15 and 16).

Table 15
Efficacy of FRAGMIN in the Prophylaxis of Deep Vein Thrombosis Following Abdominal Surgery
Indication | Dosing Regimen
Indication | FRAGMIN 2,500 units once daily subcutaneous n (%) | Placebo once daily subcutaneous n (%)
All Treated Abdominal Surgery Patients | 102 | 102
Treatment Failures in Evaluable Patients Total Thromboembolic Reactions | 4/91 (4.4) [p-value = 0.008] | 16/91 (17.6)
Proximal DVT | 0 | 5/91 (5.5)
Distal DVT | 4/91 (4.4) | 11/91 (12.1)
PE | 0 | 2/91 (2.2) [Both patients also had DVT, 1 proximal and 1 distal]

Table 16
Efficacy of FRAGMIN in the Prophylaxis of Deep Vein Thrombosis Following Abdominal Surgery
Indication | Dosing Regimen
Indication | FRAGMIN 2,500 units once daily subcutaneous n (%) | Heparin 5,000 units twice daily subcutaneous n (%)
All Treated Abdominal Surgery Patients | 195 | 196
Treatment Failures in Evaluable Patients Total Thromboembolic Reactions | 7/178 (3.9) [p-value = 0.74] | 7/174 (4)
Proximal DVT | 3/178 (1.7) | 4/174 (2.3)
Distal DVT | 3/178 (1.7) | 3/174 (1.7)
PE | 1/178 (0.6) | 0

In a third double-blind, randomized study performed in patients undergoing major abdominal surgery with malignancy, FRAGMIN 5,000 units subcutaneous once daily was compared with FRAGMIN 2,500 units subcutaneous once daily. Treatment was continued for 6 days to 8 days. A total of 1,375 patients were enrolled and treated; 679 received FRAGMIN 5,000 units and 696 received 2,500 units. The mean age of the combined groups was 71 years (range 40 years to 95 years). The majority of patients were female (51.0%). FRAGMIN 5,000 units once daily was more effective than FRAGMIN 2,500 units once daily in reducing the risk of DVT in patients undergoing abdominal surgery with malignancy (see Table 17).

Table 17
Efficacy of FRAGMIN in the Prophylaxis of Deep Vein Thrombosis Following Abdominal Surgery
Indication | Dosing Regimen
Indication | FRAGMIN 2,500 units once daily subcutaneous n (%) | FRAGMIN 5,000 units once daily subcutaneous n (%)
All Treated Abdominal Surgery Patients [Major abdominal surgery with malignancy] | 696 | 679
Treatment Failures in Evaluable Patients Total Thromboembolic Reactions | 99/656 (15.1) [p-value = 0.001] | 60/645 (9.3)
Proximal DVT | 18/657 (2.7) | 14/646 (2.2)
Distal DVT | 80/657 (12.2) | 41/646 (6.3)
PE
Fatal | 1/674 (0.1) | 1/669 (0.1)
Non-fatal | 2 | 4

14.4 Prophylaxis of Deep Vein Thrombosis in Medical Patients at Risk for Thromboembolic Complications Due to Severely Restricted Mobility During Acute Illness

In a double-blind, multi-center, randomized, placebo-controlled clinical trial, general medical patients with severely restricted mobility who were at risk of VTE were randomized to receive either FRAGMIN 5,000 units or placebo subcutaneously once daily during Days 1 to 14 of the study. These patients had an acute medical condition requiring a projected hospital stay of at least 4 days, and were confined to bed during waking hours. The study included patients with congestive heart failure (NYHA Class III or IV), acute respiratory failure not requiring ventilatory support, and the following acute conditions with at least one risk factor occurring in >1% of treated patients: acute infection (excluding septic shock), acute rheumatic disorder, acute lumbar or sciatic pain, vertebral compression, or acute arthritis of the lower extremities. Risk factors include >75 years of age, cancer, previous DVT/PE, obesity, and chronic venous insufficiency. A total of 3,681 patients were enrolled and treated: 1,848 received FRAGMIN and 1,833 received placebo. The mean age of the study population was 69 years (range 26 years to 99 years), 92.1% were white and 51.9% were female. The primary efficacy endpoint was evaluated at Day 21 and was defined as at least one of the following within Days 1 to 21 of the study: asymptomatic DVT (diagnosed by compression ultrasound), a confirmed symptomatic DVT, a confirmed pulmonary embolism or sudden death. The follow-up extended through Day 90.

When given at a dose of 5,000 units once a day subcutaneously, FRAGMIN significantly reduced the incidence of thromboembolic reactions including verified DVT by Day 21 (see Table 18). The prophylactic effect was sustained through Day 90.

Table 18
Efficacy of FRAGMIN in the Prophylaxis of Deep Vein Thrombosis in Medical Patients with Severely Restricted Mobility During Acute Illness
Indication | Dosing Regimen
Indication | FRAGMIN 5,000 units once daily subcutaneous n (%) | Placebo once daily subcutaneous n (%)
All Treated Medical Patients During Acute Illness | 1,848 | 1,833
Treatment failure in evaluable patients (Day 21) [Defined as DVT (diagnosed by compression ultrasound at Day 21 + 3), confirmed symptomatic DVT, confirmed PE or sudden death.] DVT, PE, or sudden death | 42/1,518 (2.8) [p-value = 0.0015] | 73/1,473 (5)
Total Thromboembolic Reactions (Day 21) | 37/1,513 (2.5) | 70/1,470 (4.8)
Total DVT | 32/1,508 (2.1) | 64/1,464 (4.4)
Proximal DVT | 29/1,518 (1.9) | 60/1,474 (4.1)
Symptomatic VTE | 10/1,759 (0.6) | 17/1,740 (1)
PE | 5/1,759 (0.3) | 6/1,740 (0.3)
Sudden Death | 5/1,829 (0.3) | 3/1,807 (0.2)

14.5 Patients with Cancer and Acute Symptomatic VTE

Adult Patients

In a prospective, multi-center, open-label, clinical trial, 676 patients with cancer and newly diagnosed, objectively confirmed acute deep vein thrombosis (DVT) and/or pulmonary embolism (PE) were studied. Patients were randomized to either FRAGMIN 200 units/kg subcutaneous (max 18,000 units subcutaneous daily for one month) then 150 units/kg subcutaneous (max 18,000 units) subcutaneous daily for five months (FRAGMIN arm) or FRAGMIN 200 units/kg subcutaneous (max 18,000 units) subcutaneous daily for 5 days to 7 days and oral anticoagulant for six months (OAC arm). In the OAC arm, oral anticoagulation was adjusted to maintain an INR of 2 to 3. Patients were evaluated for recurrence of symptomatic VTE every two weeks for six months.

The median age of patients was 64 years (range: 22 years to 89 years); 51.5% of patients were females; 95.3% of patients were Caucasians. Types of tumors were: gastrointestinal tract (23.7%), genito-urinary (21.5%), breast (16%), lung (13.3%), hematological tumors (10.4%), and other tumors (15.1%).

A total of 27 (8.0%) and 53 (15.7%) patients in the FRAGMIN and OAC arms, respectively, experienced at least one episode of an objectively confirmed, symptomatic DVT and/or PE during the 6-month study period. Most of the difference occurred during the first month of treatment (see Table 19). The benefit was maintained over the 6-month study period.

Table 19
Recurrent VTE in Patients with Cancer (Intention to treat population) [Three patients in the FRAGMIN arm and 5 patients in the OAC arm experienced more than 1 VTE over the 6 months study period.]
Study Period | FRAGMIN arm |  |  | OAC arm
 | FRAGMIN 200 units/kg (max. 18,000 units) subcutaneous once daily × 1 month, then 150 units/kg (max. 18,000 units) subcutaneous once daily × 5 months |  |  | FRAGMIN 200 units/kg (max 18,000 units) subcutaneous once daily × 5 days to 7 days and OAC for 6 months (target INR 2 to 3)
 | Number at Risk | Patients with VTE | % | Number at Risk | Patients with VTE | %
Total | 338 | 27 | 8 | 338 | 53 | 15.7
Week 1 | 338 | 5 | 1.5 | 338 | 8 | 2.4
Weeks 2 to 4 | 331 | 6 | 1.8 | 327 | 25 | 7.6
Weeks 5 to 28 | 307 | 16 | 5.2 | 284 | 20 | 7

In the intent-to-treat population that included all randomized patients, the primary comparison of the cumulative probability of the first VTE recurrence over the 6 months study period was statistically significant (p <0.01) in favor of the FRAGMIN arm, with most of the treatment difference evident in the first month.

Pediatric Patients

The efficacy of FRAGMIN is based on a single-arm, open-label, multi-center clinical trial in 38 pediatric patients with or without cancer and symptomatic deep vein thrombosis and/or pulmonary embolism. This study included 26 patients with an active malignancy and 12 patients without cancer. Of the 38 total patients, 3 patients were less than 2 years, 8 patients were 2 years to less than 8 years, 7 patients were 8 years to less than 12 years, and 17 patients were 12 years to less than or equal to 18 years. Patients were treated with FRAGMIN for up to 3 months, with starting doses by age and weight.

The efficacy of FRAGMIN was established by the achievement of therapeutic anti-Xa levels by Day 7 of therapy during the dose adjustment period and supported by the number of patients with lack of VTE progression or new VTE.

The efficacy population included pediatric patients who achieved a therapeutic anti-Xa level (0.5 mg per day to 1 units/mL) in the 7-day dose adjustment period (N = 34). The median doses of FRAGMIN (units/kg) required to achieve a therapeutic anti-Xa level during the dose adjustment period are presented in Table 20. Therapeutic anti-Xa levels were achieved within a mean of 2.6 days (range: 1 days to 7 days).

At study completion, 21 patients (62%) achieved resolution of the qualifying VTE, 7 patients (21%) showed regression, 2 patients (6%) showed no change, and no patients showed progression of the qualifying VTE. One patient (3%) experienced a new VTE during the study while on treatment.

Table 20
Median Doses of FRAGMIN (units/kg) Associated with Therapeutic Anti-Xa Level (0.5 to 1 units/mL) by Age Cohort (N = 34)
Age Cohort | N | Median Dose (units/kg)
Greater than or equal to 8 weeks to less than 2 years | 2 | 208 units/kg
Greater than or equal to 2 years to less than 8 years | 8 | 128 units/kg
Greater than or equal to 8 years to less than 12 years | 7 | 125 units/kg
Greater than or equal to 12 years to less than or equal to 18 years | 17 | 117 units/kg

14.6 Neonatal Patients

The efficacy of FRAGMIN in neonatal patients is based on a retrospective, non-interventional, multi-center study in 16 neonatal patients with deep vein thrombosis. Of the 16 total patients, the median gestational age was 39.1 weeks and median age at first FRAGMIN dose was 13.5 days. Patients were treated with FRAGMIN for up to 3.5 months, with starting doses determined by weight.

The efficacy of FRAGMIN was established by the achievement of VTE resolution and/or completion of FRAGMIN treatment and was supported by the number of patients with lack of VTE progression or new VTE.

The efficacy population included neonatal patients who completed a treatment course of FRAGMIN and/or achieved VTE resolution. The median starting dose of FRAGMIN and the median dose (units/kg) required to achieve a therapeutic anti-Xa level during the dose adjustment period are presented in Table 21. Therapeutic anti-Xa levels were documented for 8 of the 16 patients.

At the end of follow-up, resolution of the baseline VTE was documented for 4 patients (25%). No patients were reported to have either partial regression of the VTE or a new VTE. Of the remaining 12 patients, 1 patient (6%) switched to another anticoagulant after 3 days for an unknown reason (no adverse events related to FRAGMIN were documented) and 11 patients (69%) were reported to have completed their course of therapy.

Table 21
Median Starting and Maintenance Doses of FRAGMIN (units/kg) in Neonatal Cohort (N = 16)
All study patients (N=16) | Start Dose (units/kg); given BID | Maintenance Dose (units/kg); given BID
Median (Range) | 154.5 (100, 475) units/kg | 345 (96, 723) units/kg

16 HOW SUPPLIED/STORAGE AND HANDLING

FRAGMIN (dalteparin sodium) injection, USP, is a sterile, aqueous, clear, colorless or straw-colored solution available as follows:

Presentation | Strength | Package Size | NDC Number
Single-dose prefilled syringe [Single-dose prefilled syringe, affixed with a 27-gauge × 1/2 inch needle and preassembled with UltraSafe Passive™ Needle Guard devices. Discard unused portion.] | 2,500 units / 0.2 mL | 10 Syringes | 0069-0195-02
Single-dose prefilled syringe [Single-dose prefilled syringe, affixed with a 27-gauge × 1/2 inch needle and preassembled with UltraSafe Passive™ Needle Guard devices. Discard unused portion.] | 5,000 units / 0.2 mL | 10 Syringes | 0069-0196-02
Single-dose prefilled syringe [Single-dose prefilled syringe, affixed with a 27-gauge × 1/2 inch needle and preassembled with UltraSafe Passive™ Needle Guard devices. Discard unused portion.] | 7,500 units / 0.3 mL | 10 Syringes | 0069-0206-02
Single-dose graduated syringe [Single-dose graduated syringe, affixed with a 27-gauge × 1/2 inch needle and preassembled with UltraSafe Passive™ Needle Guard devices. UltraSafe Passive™ Needle Guard is a trademark of Safety Syringes, Inc. Discard unused portion.] | 10,000 units / mL | 10 Syringes | 0069-0217-02
Single-dose prefilled syringe | 12,500 units / 0.5 mL | 10 Syringes | 0069-0220-02
Single-dose prefilled syringe | 15,000 units / 0.6 mL | 10 Syringes | 0069-0223-02
Single-dose prefilled syringe | 18,000 units / 0.72 mL | 10 Syringes | 0069-0228-02
Multiple-dose vial | 95,000 units / 3.8 mL (25,000 units / mL) | 3.8 mL vial | 0069-0232-01
Single-dose vial | 10,000 units / 4 mL (2,500 units / mL) | 10 vials | 0069-0253-10

STORAGE AND HANDLING

Store at 20°C to 25°C (68°F to 77°F); excursion permitted between 15°C to 30°C (59°F to 86°F) [see USP Controlled Room Temperature].

Latex Allergy: The needle shield of the prefilled syringe may contain natural rubber latex [see Dosage and Administration (2.7)].

17 PATIENT COUNSELING INFORMATION

Advise the patient to read the FDA-approved patient labeling (Patient Information).

Risk of Hemorrhage including Spinal/Epidural Hematomas

If patients have had neuraxial anesthesia or spinal puncture, and particularly, if they are taking concomitant NSAIDs, platelet inhibitors, or other anticoagulants, inform the patients to watch for signs and symptoms of spinal or epidural hematoma, such as tingling, numbness (especially in the lower limbs) and muscular weakness. If any of these symptoms occur the patient should contact his or her physician immediately.

Additionally, the use of aspirin and other NSAIDs may enhance the risk of hemorrhage. Discontinue their use prior to FRAGMIN therapy whenever possible; if co-administration is essential, the patient's clinical and laboratory status should be closely monitored [see Drug Interactions (7)].

Inform Patients:

- of the instructions for injecting FRAGMIN if their therapy is to continue after discharge from the hospitals.
- it may take them longer than usual to stop bleeding.
- they may bruise and/or bleed more easily when they are treated with FRAGMIN.
- they should report any unusual bleeding, bruising, or signs of thrombocytopenia (such as a rash of dark red spots under the skin) to their physician [see Warnings and Precautions (5.1, 5.2)].
- to tell their physicians and dentists they are taking FRAGMIN and/or any other product known to affect bleeding before any surgery is scheduled and before any new drug is taken [see Warnings and Precautions (5.1)].
- to tell their physicians and dentists of all medications they are taking, including those obtained without a prescription, such as aspirin or other NSAIDs [see Drug Interactions (7)].
- Risks are associated with benzyl alcohol in neonates, infants, and pregnant women [see Warnings and Precautions (5.3) and Use in Specific Populations (8.1)].
- to tell their physicians and care givers if they are allergic to natural rubber latex [see Dosage and Administration (2.7)].

This product's labeling may have been updated. For the most recent prescribing information, please visit www.pfizer.com.

FRAGMIN is a registered trademark of Pfizer Health AB.

LAB-0058-25.0

PRINCIPAL DISPLAY PANEL - 0.2 mL Syringe Label - 0195

0.2 mL
NDC 0069-0195-01

Fragmin®
(dalteparin sodium) Injection, USP

2,500 units/0.2 mL

For Subcutaneous Use
Single-dose prefilled syringe

Pfizer Labs
Division of Pfizer Inc.
NY, NY 10001

Rx only

PAA233623

PRINCIPAL DISPLAY PANEL - 0.2 mL Syringe Blister Pack Label - 0195

0.2 mL Single-dose prefilled syringe
NDC 0069-0195-01

Fragmin® (dalteparin sodium) Injection, USP

2,500 units/0.2 mL

For Subcutaneous Use
Rx only
PAA233721

PRINCIPAL DISPLAY PANEL - 0.2 mL Syringe Carton - 0195

NDC 0069-0195-02
Contains 10 of NDC 0069-0195-01

10 x 0.2 mL Single-dose prefilled syringes. Discard unused portion.

Fragmin®
(dalteparin sodium) Injection, USP

2,500 units/0.2 mL

For Subcutaneous Use
Sterile
Preservative Free

Pfizer
Hospital

Rx only

PRINCIPAL DISPLAY PANEL - 0.2 mL Syringe Label - 0196

0.2 mL
NDC 0069-0196-01

Fragmin®
(dalteparin sodium) Injection, USP

5,000 units/0.2 mL

For Subcutaneous Use
Single-dose prefilled syringe
Pfizer Labs
Division of Pfizer Inc.
NY, NY 10001

Rx only

PAA233624

PRINCIPAL DISPLAY PANEL - 0.2 mL Syringe Blister Pack Label - 0196

0.2 mL Single-dose prefilled syringe
NDC 0069-0196-01

Fragmin® (dalteparin sodium) Injection, USP

5,000 units/0.2 mL

For Subcutaneous Use
Rx only
PAA233722

PRINCIPAL DISPLAY PANEL - 0.2 mL Syringe Carton - 0196

NDC 0069-0196-02
Contains 10 of NDC 0069-0196-01

10 x 0.2 mL Single-dose prefilled syringes. Discard unused portion.

Fragmin®
(dalteparin sodium) Injection, USP

5,000 units/0.2 mL

For Subcutaneous Use
Sterile
Preservative Free

Pfizer
Hospital

Rx only

PRINCIPAL DISPLAY PANEL - 0.3 mL Syringe Label - 0206

0.3 mL
NDC 0069-0206-01

Fragmin®
(dalteparin sodium) Injection, USP

7,500 units/0.3 mL

For Subcutaneous Use
Single-dose prefilled syringe
Pfizer Labs
Division of Pfizer Inc.
NY, NY 10001

Rx only

PAA233625

PRINCIPAL DISPLAY PANEL - 0.3 mL Syringe Blister Pack Label - 0206

0.3 mL Single-dose prefilled syringe
NDC 0069-0206-01

Fragmin® (dalteparin sodium) Injection, USP

7,500 units/0.3 mL

For Subcutaneous Use
Rx only
PAA233723

PRINCIPAL DISPLAY PANEL - 0.3 mL Syringe Carton - 0206

NDC 0069-0206-02
Contains 10 of NDC 0069-0206-01

10 x 0.3 mL Single-dose prefilled syringes. Discard unused portion.

Fragmin®
(dalteparin sodium) Injection, USP

7,500 units/0.3 mL

For Subcutaneous Use
Sterile
Preservative Free

Pfizer
Hospital

Rx only

PRINCIPAL DISPLAY PANEL - 1 mL Syringe Label - 0217

PAA233626

Fragmin® 1 mL
(dalteparin sodium) Injection, USP

10,000
units/mL

For Subcutaneous Use
Single-dose
prefilled syringe
Pfizer Labs
Division of Pfizer Inc.
NY, NY 10001

NDC 0069-0217-01

Rx only

PRINCIPAL DISPLAY PANEL - 1 mL Syringe Blister Pack Label - 0217

1 mL Single-dose graduated syringe
NDC 0069-0217-01

Fragmin® (dalteparin sodium) Injection, USP

10,000 units/mL

For Subcutaneous Use
Rx only
PAA233724

PRINCIPAL DISPLAY PANEL - 1 mL Syringe Carton - 0217

NDC 0069-0217-02
Contains 10 of NDC 0069-0217-01

10 x 1 mL Single-dose graduated syringes. Discard unused portion.

Fragmin®
(dalteparin sodium) Injection, USP

10,000 units/mL

For Subcutaneous Use
Sterile
Preservative Free

Pfizer
Hospital

Rx only

PRINCIPAL DISPLAY PANEL - 0.5 mL Syringe Label - 0220

0.5 mL NDC 0069-0220-01

Fragmin®
(dalteparin sodium) Injection, USP

12,500 units/0.5 mL

For Subcutaneous Use
Single-dose prefilled syringe
Pfizer Labs
Division of Pfizer Inc.
NY, NY 10001

Rx only

PAA233627

PRINCIPAL DISPLAY PANEL - 0.5 mL Syringe Blister Pack Label - 0220

0.5 mL Single-dose prefilled syringe
NDC 0069-0220-01

Fragmin® (dalteparin sodium) Injection, USP

12,500 units/0.5 mL

For Subcutaneous Use
Rx only
PAA233725

PRINCIPAL DISPLAY PANEL - 0.5 mL Syringe Carton - 0220

NDC 0069-0220-02
Contains 10 of NDC 0069-0220-01

10 x 0.5 mL Single-dose prefilled syringes. Discard unused portion.

Fragmin®
(dalteparin sodium) Injection, USP

12,500 units/0.5 mL

For Subcutaneous Use
Sterile
Preservative Free

Pfizer
Hospital

Rx only

PRINCIPAL DISPLAY PANEL - 0.6 mL Syringe Label-0223

0.6 mL NDC 0069-0223-01

Fragmin®
(dalteparin sodium) Injection, USP

15,000 units/0.6 mL

For Subcutaneous Use
Single-dose prefilled syringe
Pfizer Labs
Division of Pfizer Inc.
NY, NY 10001

Rx only

PAA233629

PRINCIPAL DISPLAY PANEL - 0.6 mL Syringe Blister Pack Label - 0223

0.6 mL Single-dose prefilled syringe
NDC 0069-0223-01

Fragmin® (dalteparin sodium) Injection, USP

15,000 units/0.6 mL

For Subcutaneous Use
Rx only
PAA233727

PRINCIPAL DISPLAY PANEL - 0.6 mL Syringe Carton - 0223

NDC 0069-0223-02
Contains 10 of NDC 0069-0223-01

10 x 0.6 mL Single-dose prefilled syringes. Discard unused portion.

Fragmin®
(dalteparin sodium) Injection, USP

15,000 units/0.6 mL

For Subcutaneous Use
Sterile
Preservative Free

Pfizer
Hospital

Rx only

PRINCIPAL DISPLAY PANEL - 0.72 mL Syringe Label - 0228

0.72 mL
NDC 0069-0228-01

Fragmin®
(dalteparin sodium) Injection, USP

18,000 units/0.72 mL

For Subcutaneous Use
Single-dose prefilled syringe

Pfizer Labs
Division of Pfizer Inc.
NY, NY 10001

Rx only

PAA233628

PRINCIPAL DISPLAY PANEL - 0.72 mL Syringe Blister Pack Label - 0228

0.72 mL Single-dose prefilled syringe
NDC 0069-0228-01

Fragmin® (dalteparin sodium) Injection, USP

18,000 units/0.72 mL

For Subcutaneous Use
Rx only
PAA233726

PRINCIPAL DISPLAY PANEL - 0.72 mL Syringe Carton - 0228

NDC 0069-0228-02
Contains 10 of NDC 0069-0228-01

10 x 0.72 mL Single-dose prefilled syringes, Discard unused portion.

Fragmin®
(dalteparin sodium) Injection, USP

18,000 units/0.72 mL

For Subcutaneous Use
Sterile
Preservative Free

Pfizer
Hospital

Rx only

PRINCIPAL DISPLAY PANEL - 95,000 IU Vial Label - 0232

NDC 0069-0232-01

3.8 mL Multiple-dose vial

Fragmin®
(dalteparin sodium) Injection, USP

95,000 units/3.8 mL
(25,000 units/mL)

For Subcutaneous Use
Rx only

PRINCIPAL DISPLAY PANEL - 95,000 IU Vial Carton - 0232

NDC 0069-0232-01

3.8 mL Multiple-dose vial

Fragmin®
(dalteparin sodium) Injection, USP

95,000 units/3.8 mL
(25,000 units/mL)

For Subcutaneous Use
Sterile
Contains benzyl alcohol as a
preservative.

Pfizer
Hospital

Rx only

PRINCIPAL DISPLAY PANEL - 10,000 IU Vial Label - 0253

NDC 0069-0253-01

4 mL single-dose vial

Fragmin®
(dalteparin sodium) Injection, USP

10,000 IU/4 mL
(2,500 IU/mL)

For subcutaneous injection

Rx only

PRINCIPAL DISPLAY PANEL - 10,000 IU Vial Carton - 0253

NDC 0069-0253-10

Ten 4 mL single-dose vials

Fragmin®
(dalteparin sodium) Injection, USP

10,000 IU/4 mL
(2,500 IU/mL)

For subcutaneous injection
Sterile

Rx only

Pfizer
Hospital